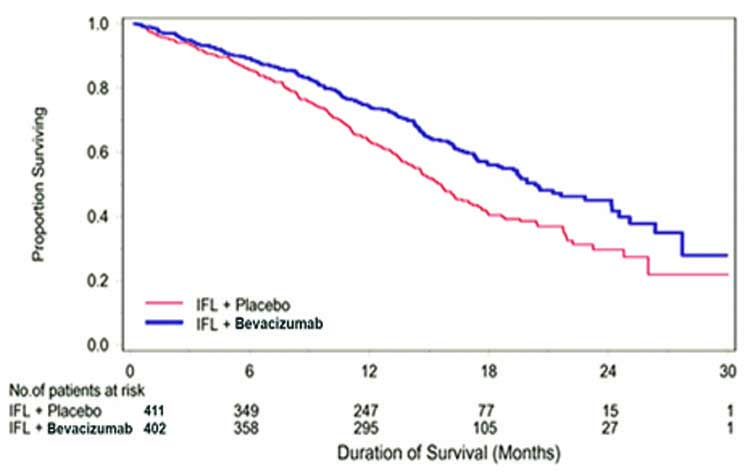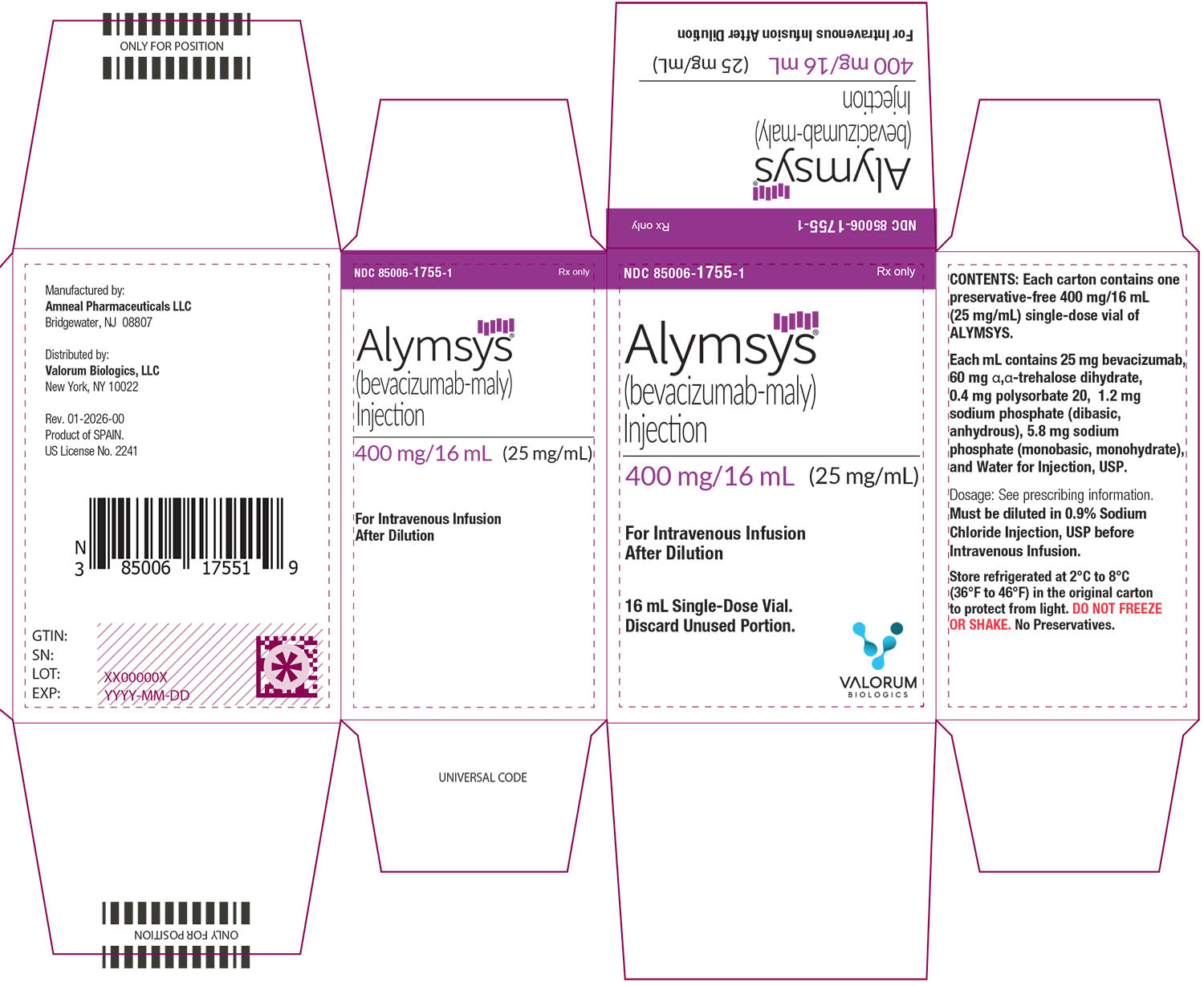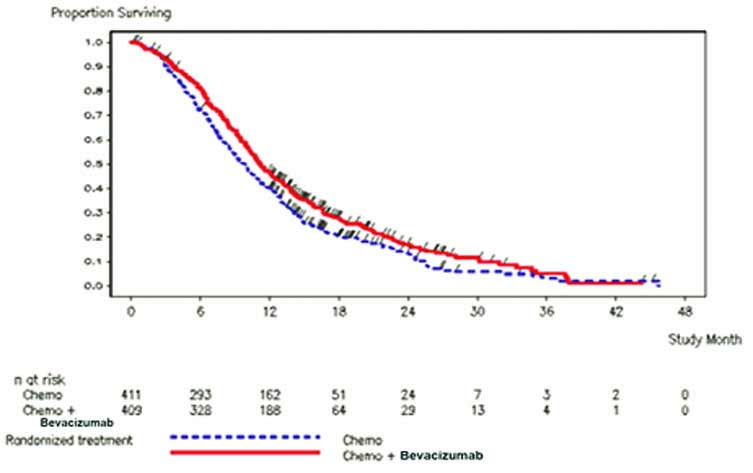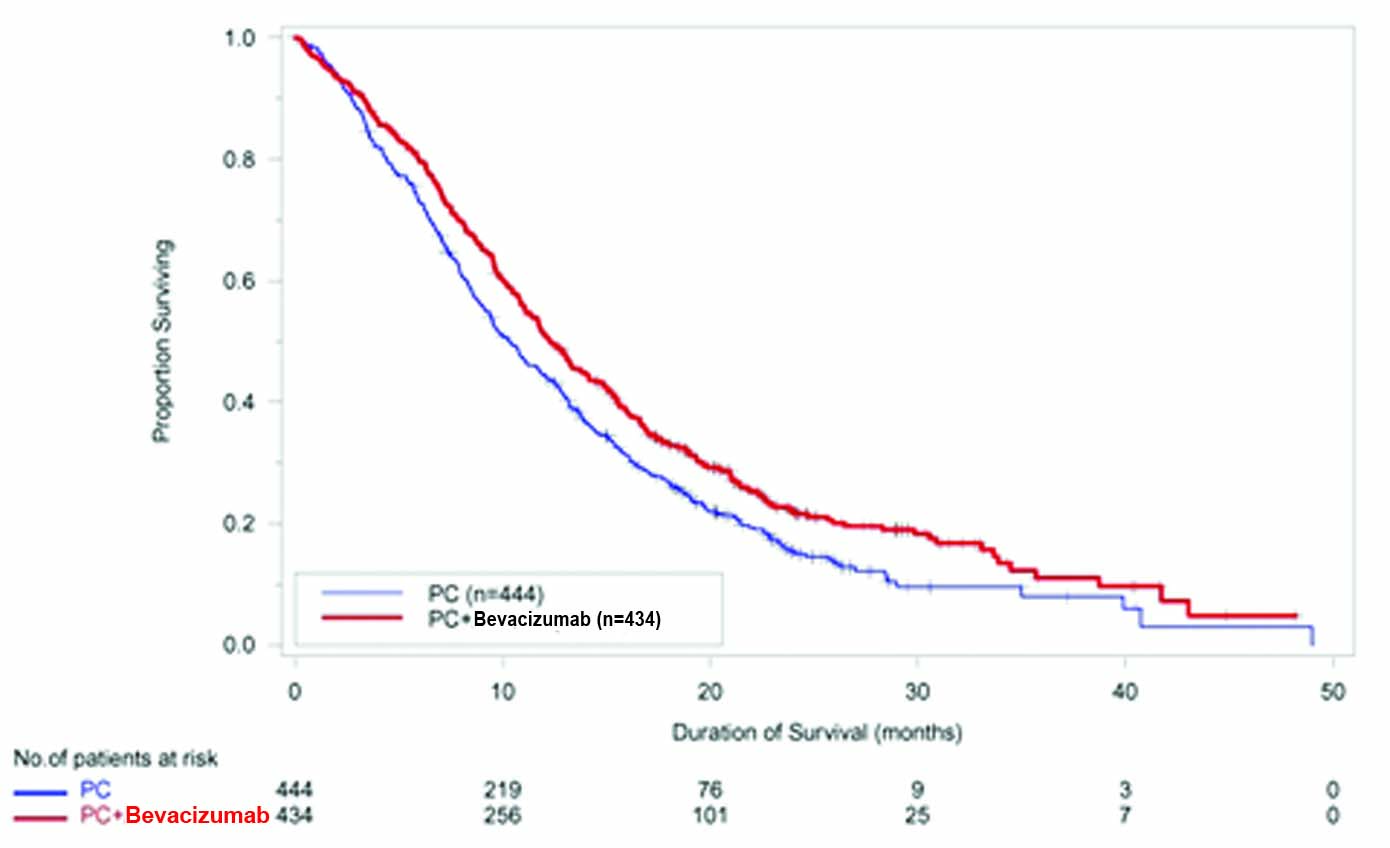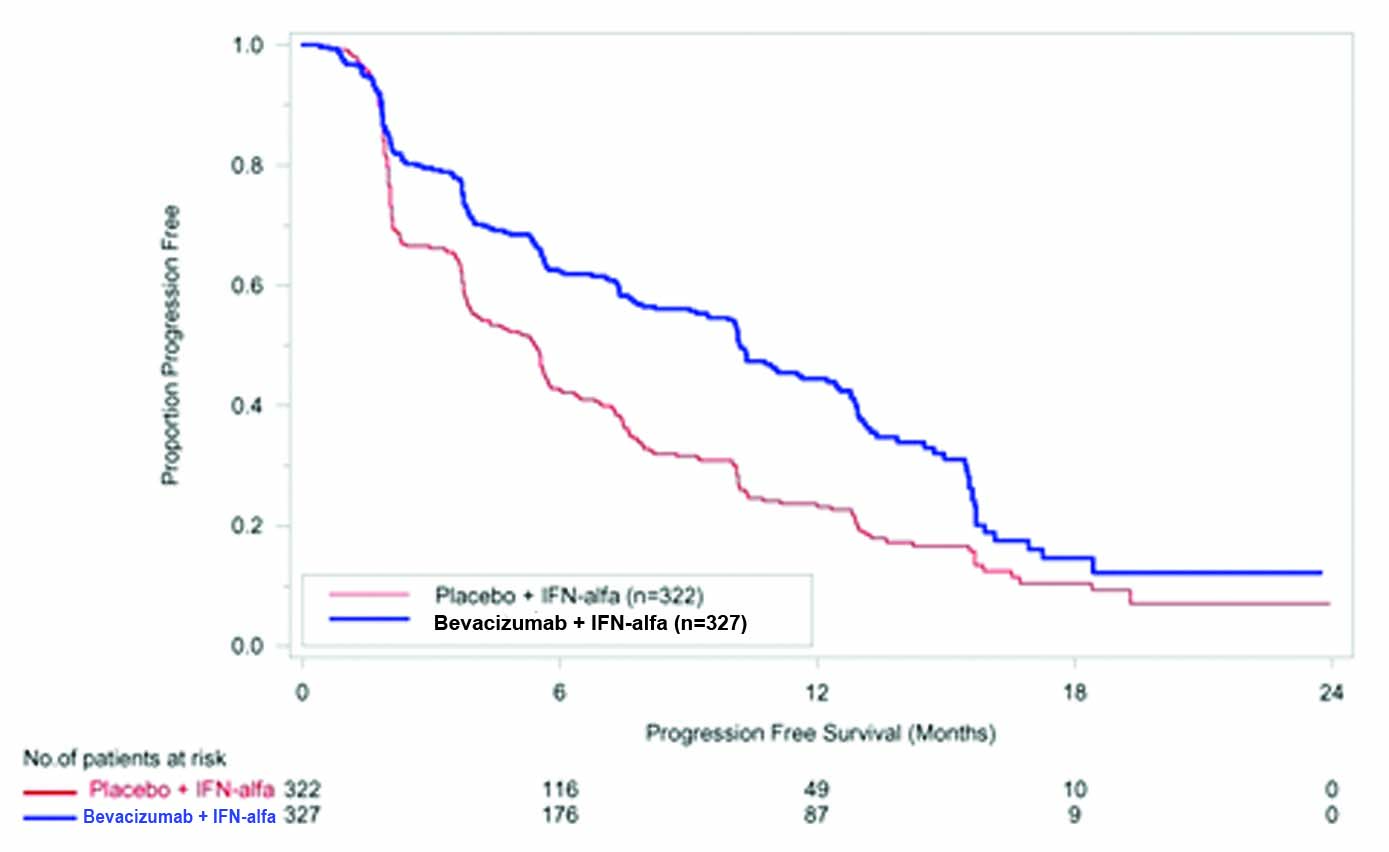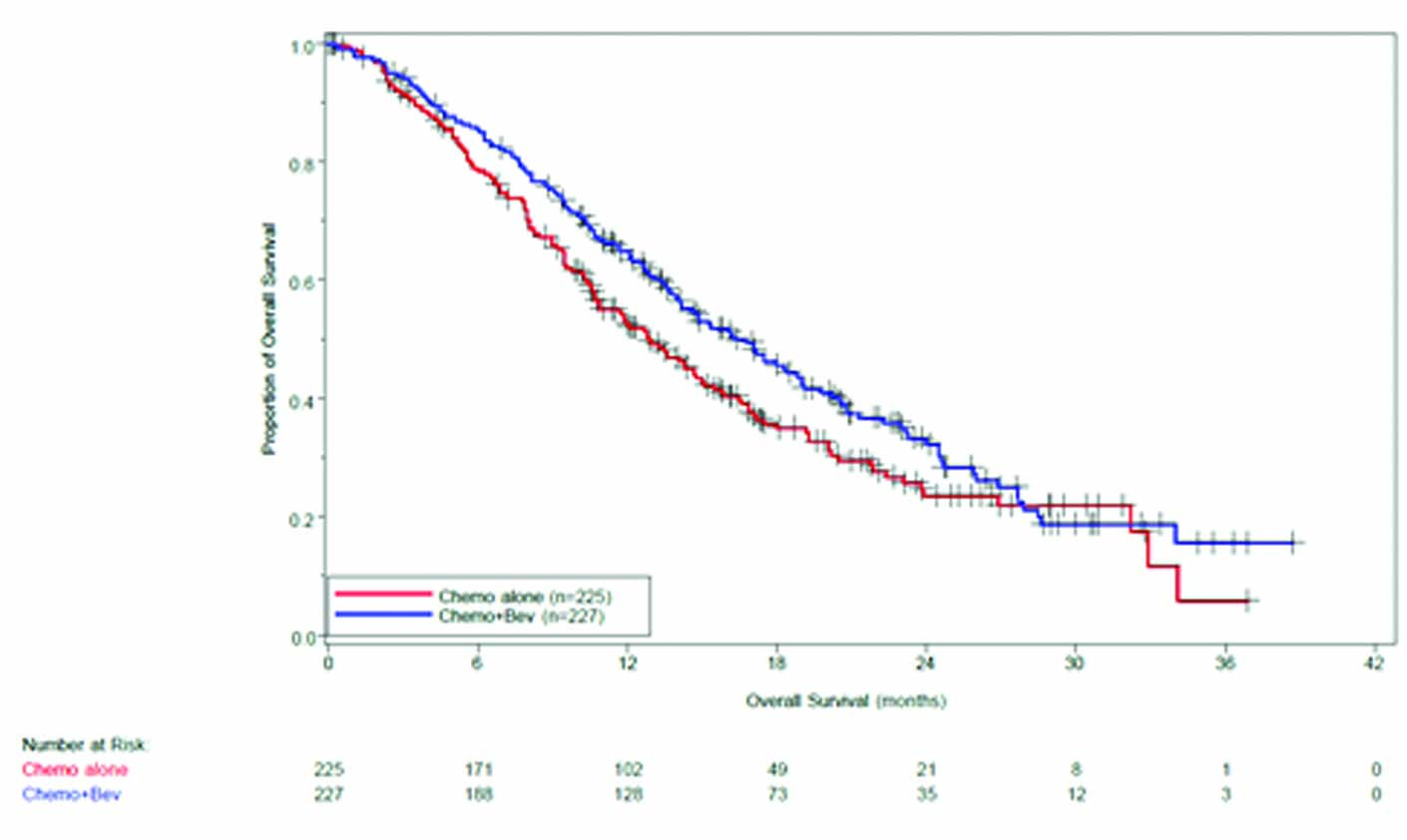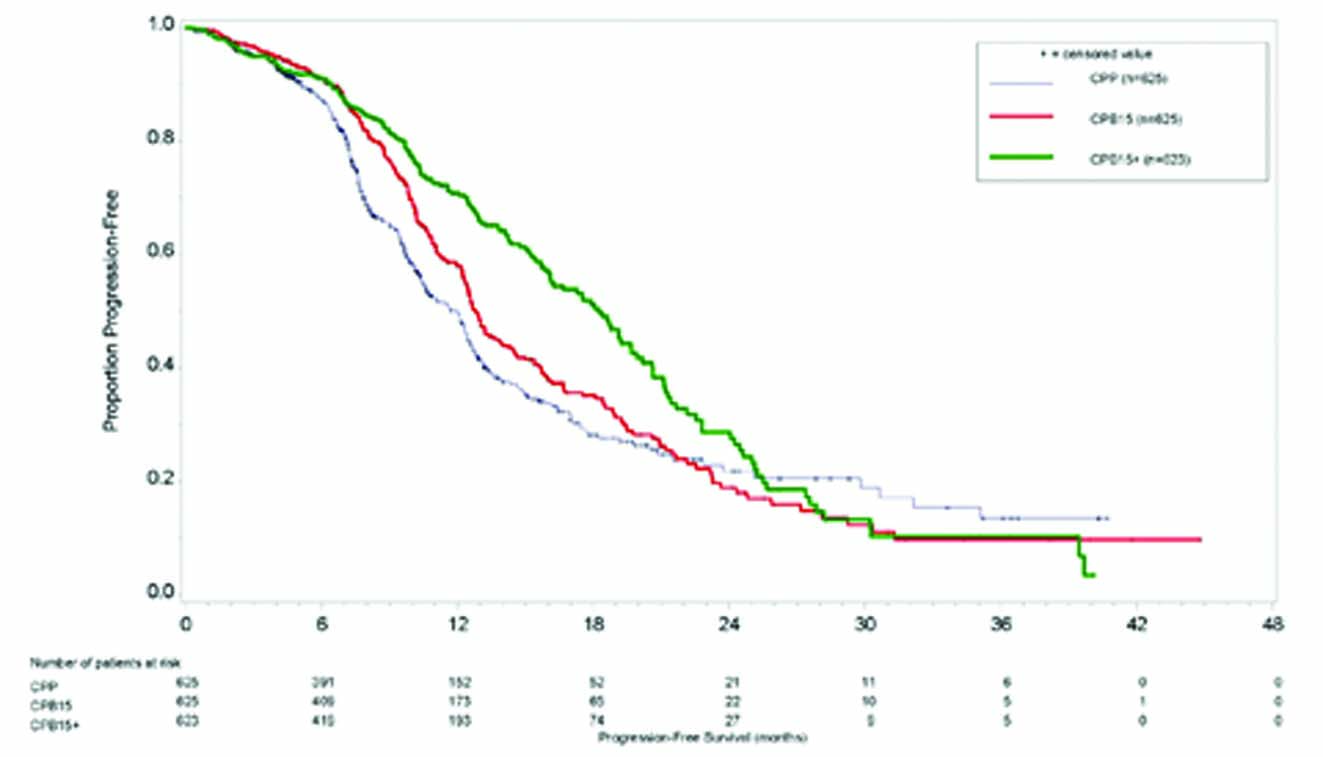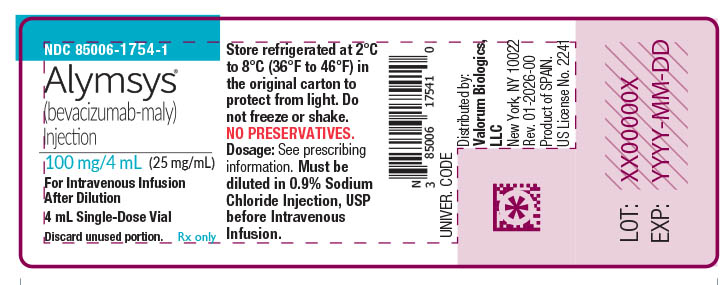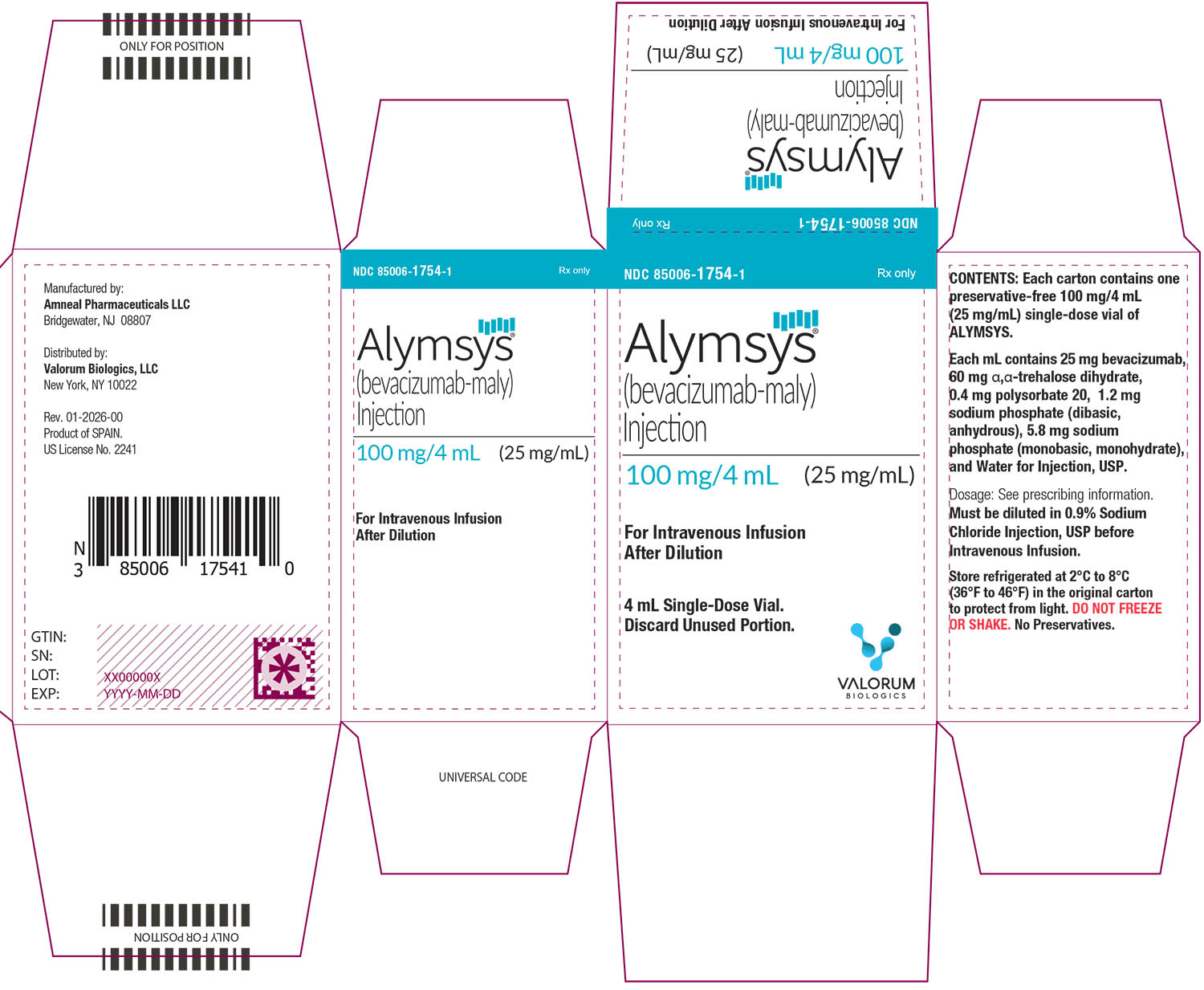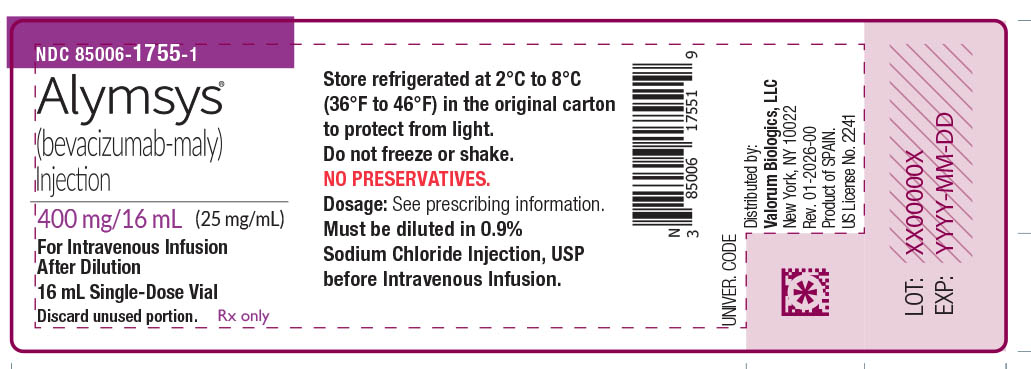 DRUG LABEL: ALYMSYS
NDC: 85006-1754 | Form: INJECTION, SOLUTION
Manufacturer: Valorum Biologics, LLC
Category: prescription | Type: HUMAN PRESCRIPTION DRUG LABEL
Date: 20260127

ACTIVE INGREDIENTS: BEVACIZUMAB-MALY 100 mg/4 mL
INACTIVE INGREDIENTS: TREHALOSE DIHYDRATE 240 mg/4 mL; POLYSORBATE 20 1.6 mg/4 mL; SODIUM PHOSPHATE, DIBASIC, ANHYDROUS 4.8 mg/4 mL; SODIUM PHOSPHATE, MONOBASIC, MONOHYDRATE 23.2 mg/4 mL; WATER

HIGHLIGHTS OF PRESCRIBING INFORMATION

These highlights do not include all the information needed to use ALYMSYSsafely and effectively. See full prescribing information for ALYMSYS. ALYMSYS® (bevacizumab-maly) injection, for intravenous use Initial U.S. Approval: 2022 ALYMSYS (bevacizumab-maly) is biosimilar* to AVASTIN (bevacizumab)

1 INDICATIONS AND USAGE

Alymsys is a vascular endothelial growth factor inhibitor indicated for the treatment of:

- Metastatic colorectal cancer, in combination with intravenous fluorouracil-based chemotherapy for first- or second-line treatment. (1.1)
- Metastatic colorectal cancer, in combination with fluoropyrimidine-irinotecan- or fluoropyrimidine-oxaliplatin-based chemotherapy for second-line treatment in patients who have progressed on a first-line bevacizumab product-containing regimen. (1.1)

Limitations of Use: Alymsys is not indicated for adjuvant treatment of colon cancer. (1.1)

- Unresectable, locally advanced, recurrent or metastatic non-squamous non-small cell lung cancer, in combination with carboplatin and paclitaxel for first-line treatment. (1.2)
- Recurrent glioblastoma in adults. (1.3)
- Metastatic renal cell carcinoma in combination with interferon alfa. (1.4)
- Persistent, recurrent, or metastatic cervical cancer, in combination with paclitaxel and cisplatin, or paclitaxel and topotecan. (1.5)

- Epithelial ovarian, fallopian tube, or primary peritoneal cancer in combination with paclitaxel, pegylated liposomal doxorubicin, or topotecan for platinum-resistant recurrent disease who received no more than 2 prior chemotherapy regimens (1.6)

2 DOSAGE AND ADMINISTRATION

Withhold for at least 28 days prior to elective surgery. Do not administer Alymsys for 28 days following major surgery and until adequate wound healing. (2.1)

Metastatic colorectal cancer (2.2)

- 5 mg/kg every 2 weeks with bolus-IFL
- 10 mg/kg every 2 weeks with FOLFOX4
- 5 mg/kg every 2 weeks or 7.5 mg/kg every 3 weeks with fluoropyrimidine-irinotecan- or fluoropyrimidine-oxaliplatin-based chemotherapy after progression on a first-line bevacizumab product-containing regimen

First-line non−squamous non−small cell lung cancer (2.3)

- 15 mg/kg every 3 weeks with carboplatin and paclitaxel
  Recurrent glioblastoma (2.4)
- 10 mg/kg every 2 weeks
  Metastatic renal cell carcinoma (2.5)
- 10 mg/kg every 2 weeks with interferon alfa
  Persistent, recurrent, or metastatic cervical cancer (2.6)
- 15 mg/kg every 3 weeks with paclitaxel and cisplatin, or paclitaxel and topotecan
  Platinum-resistant recurrent epithelial ovarian, fallopian tube or primary peritoneal cancer (2.7)
- 10 mg/kg every 2 weeks with paclitaxel, pegylated liposomal doxorubicin, or topotecan given every week
- 15 mg/kg every 3 weeks with topotecan given every 3 weeks

Administer as an intravenous infusion (2.9)

3 DOSAGE FORMS AND STRENGTHS

Injection: 100 mg/4 mL (25 mg/mL) or 400 mg/16 mL (25 mg/mL) in a single-dose vial (3)

4 CONTRAINDICATIONS

None (4)

5 WARNINGS AND PRECAUTIONS

- Gastrointestinal Perforations and Fistula: Discontinue for gastrointestinal perforations, tracheoesophageal fistula, grade 4 fistula, or fistula formation involving any organ (5.1)
- Surgery and Wound Healing Complications: In patients who experience wound healing complications during Alymsys treatment, withhold Alymsys until adequate wound healing. Withhold for at least 28 days prior to elective surgery. Do not administer Alymsys for at least 28 days following a major surgery, and until adequate wound healing. The safety of resumption of bevacizumab products after resolution of wound healing complication has not been established. Discontinue for wound healing complication of necrotizing fasciitis. (5.2)
- Hemorrhage: Severe or fatal hemorrhages have occurred. Do not administer for recent hemoptysis. Discontinue for Grade 3-4 hemorrhage (5.3)
- Arterial Thromboembolic Events (ATE): Discontinue for severe ATE. (5.4)
- Venous Thromboembolic Events (VTE): Discontinue for Grade 4 VTE. (5.5)
- Hypertension: Monitor blood pressure and treat hypertension. Withhold if not medically controlled; resume once controlled. Discontinue for hypertensive crisis or hypertensive encephalopathy. (5.6)
- Posterior Reversible Encephalopathy Syndrome (PRES): Discontinue. (5.7)
- Renal Injury and Proteinuria: Monitor urine protein. Discontinue for nephrotic syndrome. Withhold until less than 2 grams of protein in urine. (5.8)
- Infusion-Related Reactions: Decrease rate for infusion-related reactions. Discontinue for severe infusion-related reactions and administer medical therapy. (5.9)
- Embryo-Fetal Toxicity: May cause fetal harm. Advise females of potential risk to fetus and need for use of effective contraception. (5.10, 8.1, 8.3)
- Ovarian Failure: Advise females of the potential risk. (5.11, 8.3)
- Congestive Heart Failure (CHF): Discontinue Alymsys in patients who develop CHF. (5.12)

6 ADVERSE REACTIONS

Most common adverse reactions incidence (incidence > 10%) are epistaxis, headache, hypertension, rhinitis, proteinuria, taste alteration, dry skin, hemorrhage, lacrimation disorder, back pain and exfoliative dermatitis. (6.1)

To report SUSPECTED ADVERSE REACTIONS, contact Valorum Biologics, LLC at 1-844-576-2709 or FDA at 1-800-FDA-1088 or www.fda.gov/medwatch.

8 USE IN SPECIFIC POPULATIONS

Lactation: Advise not to breastfeed. (8.2)

See 17 for PATIENT COUNSELING INFORMATION.

*Biosimilar means that the biological product is approved based on data demonstrating that it is highly similar to an FDA-approved biological product, known as a reference product, and that there are no clinically meaningful differences between the biosimilar product and the reference product. Biosimilarity of ALYMSYS has been demonstrated for the condition(s) of use (e.g. indication(s), dosing regimen(s)), strength(s), dosage form(s), and route(s) of administration described in its Full Prescribing Information.

FULL PRESCRIBING INFORMATION

1 INDICATIONS AND USAGE

1.1 Metastatic Colorectal Cancer

Alymsys, in combination with intravenous fluorouracil-based chemotherapy, is indicated for the first-or second-line treatment of patients with metastatic colorectal cancer (mCRC).

Alymsys, in combination with fluoropyrimidine-irinotecan- or fluoropyrimidine-oxaliplatin-based chemotherapy, is indicated for the second-line treatment of patients with mCRC who have progressed on a first-line bevacizumab product-containing regimen.

Limitations of Use: Alymsys is not indicated for adjuvant treatment of colon cancer [see Clinical Studies (14.2)].

1.2 First-Line Non-Squamous Non–Small Cell Lung Cancer

Alymsys, in combination with carboplatin and paclitaxel, is indicated for the first-line treatment of patients with unresectable, locally advanced, recurrent or metastatic non–squamous non–small cell lung cancer (NSCLC).

1.3 Recurrent Glioblastoma

Alymsys is indicated for the treatment of recurrent glioblastoma (GBM) in adults.

1.4 Metastatic Renal Cell Carcinoma

Alymsys, in combination with interferon alfa, is indicated for the treatment of metastatic renal cell carcinoma (mRCC).

1.5 Persistent, Recurrent, or Metastatic Cervical Cancer

Alymsys, in combination with paclitaxel and cisplatin or paclitaxel and topotecan, is indicated for the treatment of patients with persistent, recurrent, or metastatic cervical cancer.

1.6 Epithelial Ovarian, Fallopian Tube, or Primary Peritoneal Cancer

Alymsys, in combination with paclitaxel, pegylated liposomal doxorubicin, or topotecan, is indicated for the treatment of patients with platinum-resistant recurrent epithelial ovarian, fallopian tube or primary peritoneal cancer who received no more than 2 prior chemotherapy regimens.

2 DOSAGE AND ADMINISTRATION

2.1 Important Administration Information

Withhold for at least 28 days prior to elective surgery. Do not administer Alymsys until at least 28 days following major surgery and until adequate wound healing.

2.2 Metastatic Colorectal Cancer

The recommended dosage when Alymsys is administered in combination with intravenous fluorouracil-based chemotherapy is:

- 5 mg/kg intravenously every 2 weeks in combination with bolus-IFL.
- 10 mg/kg intravenously every 2 weeks in combination with FOLFOX4.
- 5 mg/kg intravenously every 2 weeks or 7.5 mg/kg intravenously every 3 weeks in combination with fluoropyrimidine-irinotecan- or fluoropyrimidine-oxaliplatin-based chemotherapy in patients who have progressed on a first-line bevacizumab product-containing regimen.

2.3 First-Line Non-Squamous Non-Small Cell Lung Cancer

The recommended dosage is 15 mg/kg intravenously every 3 weeks in combination with carboplatin and paclitaxel.

2.4 Recurrent Glioblastoma

The recommended dosage is 10 mg/kg intravenously every 2 weeks.

2.5 Metastatic Renal Cell Carcinoma

The recommended dosage is 10 mg/kg intravenously every 2 weeks in combination with interferon alfa.

2.6 Persistent, Recurrent, or Metastatic Cervical Cancer

The recommended dosage is 15 mg/kg intravenously every 3 weeks in combination with paclitaxel and cisplatin or in combination with paclitaxel and topotecan.

2.7 Epithelial Ovarian, Fallopian Tube or Primary Peritoneal Cancer

Recurrent Disease

Platinum Resistant

The recommended dosage is 10 mg/kg intravenously every 2 weeks in combination with paclitaxel, pegylated liposomal doxorubicin, or topotecan (every week).

The recommended dosage is 15 mg/kg intravenously every 3 weeks in combination with topotecan (every 3 weeks).

2.8 Dosage Modifications for Adverse Reactions

Table 1 describes dosage modifications for specific adverse reactions. No dose reductions for Alymsys are recommended.

Table 1: Dosage Modifications for Adverse Reactions
Adverse Reaction | Severity | Dosage Modification
Gastrointestinal Perforations and Fistulae [see Warnings and Precautions (5.1)]. | - Gastrointestinal perforation, any grade - Tracheoesophageal fistula, any grade - Fistula, Grade 4 - Fistula formation involving any internal organ | Discontinue Alymsys
Wound Healing Complications [see Warnings and Precautions (5.2)]. | - Any | Withhold Alymsys until adequate wound healing. The safety of resumption of bevacizumab products after resolution of wound healing complications has not been established.
Wound Healing Complications [see Warnings and Precautions (5.2)]. | - Necrotizing fasciitis | Discontinue Alymsys
Hemorrhage [see Warnings and Precautions (5.3)]. | - Grade 3 or 4 | Discontinue Alymsys
Hemorrhage [see Warnings and Precautions (5.3)]. | - Recent history of hemoptysis of 1/2 teaspoon (2.5 mL) or more | Withhold Alymsys
Thromboembolic Events [see Warnings and Precautions (5.4, 5.5)]. | - Arterial thromboembolism, severe | Discontinue Alymsys
Thromboembolic Events [see Warnings and Precautions (5.4, 5.5)]. | - Venous thromboembolism, Grade 4 | Discontinue Alymsys
Hypertension [see Warnings and Precautions (5.6)]. | - Hypertensive crisis - Hypertensive encephalopathy | Discontinue Alymsys
Hypertension [see Warnings and Precautions (5.6)]. | - Hypertension, severe | Withhold Alymsys if not controlled with medical management; resume once controlled
Posterior Reversible Encephalopathy Syndrome (PRES) [see Warnings and Precautions (5.7)]. | - Any | Discontinue Alymsys
Renal Injury and Proteinuria [see Warnings and Precautions (5.8)]. | - Nephrotic syndrome | Discontinue Alymsys
Renal Injury and Proteinuria [see Warnings and Precautions (5.8)]. | - Proteinuria greater than or equal to 2 grams per 24 hours in absence of nephrotic syndrome | Withhold Alymsys until proteinuria less than 2 grams per 24 hours
Infusion-Related Reactions [see Warnings and Precautions (5.9)]. | - Severe | Discontinue Alymsys
Infusion-Related Reactions [see Warnings and Precautions (5.9)]. | - Clinically significant | Interrupt infusion; resume at a decreased rate of infusion after symptoms resolve
Infusion-Related Reactions [see Warnings and Precautions (5.9)]. | - Mild, clinically insignificant | Decrease infusion rate
Congestive Heart Failure [see Warnings and Precautions (5.12)]. | Any | Discontinue Alymsys

2.9 Preparation and Administration

Preparation

- Use appropriate aseptic technique.
- Visually inspect vial for particulate matter and discoloration prior to preparation for administration. Discard vial if solution is cloudy, discolored or contains particulate matter.
- Withdraw necessary amount of Alymsys and dilute in a total volume of 100 mL of 0.9% Sodium Chloride Injection, USP. DO NOT ADMINISTER OR MIX WITH DEXTROSE SOLUTION.
- Discard any unused portion left in a vial, as the product contains no preservatives.
- Store diluted Alymsys solution at 2°C to 8°C (36°F to 46°F) for up to 12 hours.
- No incompatibilities between Alymsys and polyvinylchloride or polyolefin bags have been observed.

Administration

- Administer as an intravenous infusion.
- First infusion: Administer infusion over 90 minutes.
- Subsequent infusions: Administer second infusion over 60 minutes if first infusion is tolerated. Administer all subsequent infusions over 30 minutes if second infusion over 60 minutes is tolerated.

3 DOSAGE FORMS AND STRENGTHS

Injection: 100 mg/4 mL (25 mg/mL) or 400 mg/16 mL (25 mg/mL) clear to slightly opalescent, colorless to pale brown solution in a single-dose vial.

4 CONTRAINDICATIONS

None.

5 WARNINGS AND PRECAUTIONS

5.1 Gastrointestinal Perforations and Fistulae

Serious, and sometimes fatal, gastrointestinal perforation occurred at a higher incidence in patients receiving bevacizumab products compared to patients receiving chemotherapy. The incidence ranged from 0.3% to 3% across clinical studies, with the highest incidence in patients with a history of prior pelvic radiation. Perforation can be complicated by intra-abdominal abscess, fistula formation, and the need for diverting ostomies. The majority of perforations occurred within 50 days of the first dose [see Adverse Reactions (6.1)].

Serious fistulae (including, tracheoesophageal, bronchopleural, biliary, vaginal, renal and bladder sites) occurred at a higher incidence in patients receiving bevacizumab products compared to patients receiving chemotherapy. The incidence ranged from < 1% to 1.8% across clinical studies, with the highest incidence in patients with cervical cancer. The majority of fistulae occurred within 6 months of the first dose. Patients who develop a gastrointestinal vaginal fistula may also have a bowel obstruction and require surgical intervention, as well as a diverting ostomy.

Avoid Alymsys in patients with ovarian cancer who have evidence of recto-sigmoid involvement by pelvic examination or bowel involvement on CT scan or clinical symptoms of bowel obstruction. Discontinue in patients who develop gastrointestinal perforation, tracheoesophageal fistula or any Grade 4 fistula. Discontinue in patients with fistula formation involving any internal organ.

5.2 Surgery and Wound Healing Complications

In a controlled clinical study in which bevacizumab was not administered within 28 days of major surgical procedures, the incidence of wound healing complications, including serious and fatal complications, was 15% in patients with mCRC who underwent surgery while receiving bevacizumab and 4% in patients who did not receive bevacizumab. In a controlled clinical study in patients with relapsed or recurrent GBM, the incidence of wound healing events was 5% in patients who received bevacizumab and 0.7% in patients who did not receive bevacizumab [see Adverse Reactions (6.1)].

In patients who experience wound healing complications during Alymsys treatment, withhold Alymsys until adequate wound healing. Withhold for at least 28 days prior to elective surgery. Do not administer for at least 28 days following major surgery and until adequate wound healing. The safety of resumption of bevacizumab products after resolution of wound healing complications has not been established [see Dosage and Administration (2.8)].

Necrotizing fasciitis including fatal cases, has been reported in patients receiving bevacizumab, usually secondary to wound healing complications, gastrointestinal perforation or fistula formation. Discontinue Alymsys in patients who develop necrotizing fasciitis.

5.3 Hemorrhage

Bevacizumab products can result in two distinct patterns of bleeding: minor hemorrhage, which is most commonly Grade 1 epistaxis, and serious hemorrhage, which in some cases has been fatal. Severe or fatal hemorrhage, including hemoptysis, gastrointestinal bleeding, hematemesis, CNS hemorrhage, epistaxis, and vaginal bleeding, occurred up to 5-fold more frequently in patients receiving bevacizumab compared to patients receiving chemotherapy alone. Across clinical studies, the incidence of Grades 3 to 5 hemorrhagic events ranged from 0.4% to 7% in patients receiving bevacizumab [see Adverse Reactions (6.1)].

Serious or fatal pulmonary hemorrhage occurred in 31% of patients with squamous NSCLC and 4% of patients with non-squamous NSCLC receiving bevacizumab with chemotherapy compared to none of the patients receiving chemotherapy alone.

Do not administer Alymsys to patients with recent history of hemoptysis of 1/2 teaspoon or more of red blood. Discontinue in patients who develop a Grades 3 to 4 hemorrhage.

5.4 Arterial Thromboembolic Events

Serious, sometimes fatal, arterial thromboembolic events (ATE) including cerebral infarction, transient ischemic attacks, myocardial infarction, and angina, occurred at a higher incidence in patients receiving bevacizumab compared to patients receiving chemotherapy. Across clinical studies, the incidence of Grades 3 - 5 ATE was 5% in patients receiving bevacizumab with chemotherapy compared to ≤2% in patients receiving chemotherapy alone; the highest incidence occurred in patients with GBM. The risk of developing ATE was increased in patients with a history of arterial thromboembolism, diabetes, or >65 years [see Use in Specific Populations (8.5)].

Discontinue in patients who develop a severe ATE. The safety of reinitiating bevacizumab products after an ATE is resolved is not known.

5.5 Venous Thromboembolic Events

An increased risk of venous thromboembolic events (VTE) was observed across clinical studies [see Adverse Reactions (6.1)]. In Study GOG-0240, Grades 3 to 4 VTE occurred in 11% of patients receiving bevacizumab with chemotherapy compared with 5% of patients receiving chemotherapy alone. In EORTC 26101, the incidence of Grades 3 to 4 VTE was 5% in patients receiving bevacizumab with chemotherapy compared to 2% in patients receiving chemotherapy alone.

Discontinue Alymsys in patients with a Grade 4 VTE, including pulmonary embolism.

5.6 Hypertension

Severe hypertension occurred at a higher incidence in patients receiving bevacizumab products as compared to patients receiving chemotherapy alone. Across clinical studies, the incidence of Grades 3 - 4 hypertension ranged from 5% to 18%.

Monitor blood pressure every two to three weeks during treatment with Alymsys. Treat with appropriate anti-hypertensive therapy and monitor blood pressure regularly. Continue to monitor blood pressure at regular intervals in patients with Alymsys -induced or -exacerbated hypertension after discontinuing Alymsys. Withhold Alymsys in patients with severe hypertension that is not controlled with medical management; resume once controlled with medical management. Discontinue in patients who develop hypertensive crisis or hypertensive encephalopathy.

5.7 Posterior Reversible Encephalopathy Syndrome

Posterior reversible encephalopathy syndrome (PRES) was reported in <0.5% of patients across clinical studies. The onset of symptoms occurred from 16 hours to 1 year after the first dose. PRES is a neurological disorder which can present with headache, seizure, lethargy, confusion, blindness and other visual and neurologic disturbances. Mild to severe hypertension may be present. Magnetic resonance imaging is necessary to confirm the diagnosis of PRES.

Discontinue Alymsys in patients who develop PRES. Symptoms usually resolve or improve within days after discontinuing bevacizumab products, although some patients have experienced ongoing neurologic sequelae. The safety of reinitiating bevacizumab products in patients who developed PRES is not known.

5.8 Renal Injury and Proteinuria

The incidence and severity of proteinuria was higher in patients receiving bevacizumab as compared to patients receiving chemotherapy. Grade 3 (defined as urine dipstick 4+ or > 3.5 grams of protein per 24 hours) to Grade 4 (defined as nephrotic syndrome) ranged from 0.7% to 7% in clinical studies. The overall incidence of proteinuria (all grades) was only adequately assessed in Study BO17705, in which the incidence was 20%. Median onset of proteinuria was 5.6 months (15 days to 37 months) after initiating bevacizumab. Median time to resolution was 6.1 months (95% CI: 2.8, 11.3). Proteinuria did not resolve in 40% of patients after median follow-up of 11.2 months and required discontinuation of bevacizumab in 30% of the patients who developed proteinuria [see Adverse Reactions (6.1)].

In an exploratory, pooled analysis of patients from seven randomized clinical studies, 5% of patients receiving bevacizumab with chemotherapy experienced Grades 2 - 4 (defined as urine dipstick 2+ or greater or > 1 gram of protein per 24 hours or nephrotic syndrome) proteinuria. Grades 2 to 4 proteinuria resolved in 74% of patients. Bevacizumab was reinitiated in 42% of patients. Of the 113 patients who reinitiated bevacizumab, 48% experienced a second episode of Grades 2 to 4 proteinuria.

Nephrotic syndrome occurred in <1% of patients receiving bevacizumab across clinical studies, in some instances with fatal outcome. In a published case series, kidney biopsy of 6 patients with proteinuria showed findings consistent with thrombotic microangiopathy. Results of a retrospective analysis of 5,805 patients who received bevacizumab with chemotherapy and 3,713 patients who received chemotherapy alone, showed higher rates of elevated serum creatinine levels (between 1.5 to 1.9 times baseline levels) in patients who received bevacizumab. Serum creatinine levels did not return to baseline in approximately one-third of patients who received bevacizumab.

Monitor proteinuria by dipstick urine analysis for the development or worsening of proteinuria with serial urinalyses during Alymsys therapy. Patients with a 2+ or greater urine dipstick reading should undergo further assessment with a 24-hour urine collection. Withhold for proteinuria greater than or equal to 2 grams per 24 hours and resume when less than 2 grams per 24 hours. Discontinue in patients who develop nephrotic syndrome.

Data from a postmarketing safety study showed poor correlation between UPCR (Urine Protein/Creatinine Ratio) and 24-hour urine protein [Pearson Correlation 0.39 (95% CI: 0.17, 0.57)].

5.9 Infusion-Related Reactions

Infusion-related reactions reported across clinical studies and postmarketing experience include hypertension, hypertensive crises associated with neurologic signs and symptoms, wheezing, oxygen desaturation, Grade 3 hypersensitivity, chest pain, headaches, rigors, and diaphoresis. In clinical studies, infusion-related reactions with the first dose occurred in <3% of patients and severe reactions occurred in 0.4% of patients.

Decrease the rate of infusion for mild, clinically insignificant infusion-related reactions. Interrupt the infusion in patients with clinically significant infusion-related reactions and consider resuming at a slower rate following resolution. Discontinue in patients who develop a severe infusion-related reaction and administer appropriate medical therapy (e.g., epinephrine, corticosteroids, intravenous antihistamines, bronchodilators and/or oxygen).

5.10 Embryo-Fetal Toxicity

Based on its mechanism of action and findings from animal studies, bevacizumab products may cause fetal harm when administered to pregnant women. Congenital malformations were observed with the administration of bevacizumab to pregnant rabbits during organogenesis every 3 days at a dose as low as a clinical dose of 10 mg/kg. Furthermore, animal models link angiogenesis and VEGF and VEGFR2 to critical aspects of female reproduction, embryo-fetal development, and postnatal development. Advise pregnant women of the potential risk to a fetus. Advise females of reproductive potential to use effective contraception during treatment with Alymsys and for 6 months after the last dose [see Use in Specific Populations (8.1, 8.3)].

5.11 Ovarian Failure

The incidence of ovarian failure was 34% vs. 2% in premenopausal women receiving bevacizumab with chemotherapy as compared to those receiving chemotherapy alone for adjuvant treatment of a solid tumor. After discontinuing bevacizumab, recovery of ovarian function at all time points during the post-treatment period was demonstrated in 22% of women receiving bevacizumab. Recovery of ovarian function is defined as resumption of menses, a positive serum β-HCG pregnancy test, or an FSH level < 30 mIU/mL during the post-treatment period. Long-term effects of bevacizumab products on fertility are unknown. Inform females of reproductive potential of the risk of ovarian failure prior to initiating Alymsys [see Adverse Reactions (6.1), Use in Specific Populations (8.3)].

5.12 Congestive Heart Failure (CHF)

Alymsys is not indicated for use with anthracycline-based chemotherapy. The incidence of Grade ≥ 3 left ventricular dysfunction was 1% in patients receiving bevacizumab compared to 0.6% of patients receiving chemotherapy alone. Among patients who received prior anthracycline treatment, the rate of CHF was 4% for patients receiving bevacizumab with chemotherapy as compared to 0.6% for patients receiving chemotherapy alone.

In previously untreated patients with a hematological malignancy, the incidence of CHF and decline in left ventricular ejection fraction (LVEF) were increased in patients receiving bevacizumab with anthracycline-based chemotherapy compared to patients receiving placebo with the same chemotherapy regimen. The proportion of patients with a decline in LVEF from baseline of ≥ 20% or a decline from baseline of 10% to < 50%, was 10% in patients receiving bevacizumab with chemotherapy compared to 5% in patients receiving chemotherapy alone. Time to onset of left-ventricular dysfunction or CHF was 1 to 6 months after the first dose in at least 85% of the patients and was resolved in 62% of the patients who developed CHF in the bevacizumab arm compared to 82% in the placebo arm. Discontinue Alymsys in patients who develop CHF.

6 ADVERSE REACTIONS

The following clinically significant adverse reactions are described elsewhere in the labeling:

- Gastrointestinal Perforations and Fistulae [see Warnings and Precautions (5.1)].
- Surgery and Wound Healing Complications [see Warnings and Precautions (5.2)].
- Hemorrhage [see Warnings and Precautions (5.3)].
- Arterial Thromboembolic Events [see Warnings and Precautions (5.4)].
- Venous Thromboembolic Events [see Warnings and Precautions (5.5)].
- Hypertension [see Warnings and Precautions (5.6)].
- Posterior Reversible Encephalopathy Syndrome [see Warnings and Precautions (5.7)].
- Renal Injury and Proteinuria [see Warnings and Precautions (5.8)].
- Infusion-Related Reactions [see Warnings and Precautions (5.9)].
- Ovarian Failure [see Warnings and Precautions (5.11)].
- Congestive Heart Failure [see Warnings and Precautions (5.12)].

6.1 Clinical Trials Experience

Because clinical studies are conducted under widely varying conditions, adverse reaction rates observed in the clinical studies of a drug cannot be directly compared to rates in the clinical studies of another drug and may not reflect the rates observed in practice.

The safety data in Warnings and Precautions and described below reflect exposure to bevacizumab in 4,463 patients including those with mCRC (AVF2107g, E3200), non-squamous NSCLC (E4599), GBM (EORTC 26101), mRCC (BO17705), cervical cancer (GOG-0240), epithelial ovarian, fallopian tube, or primary peritoneal cancer (MO22224), or other cancers at the recommended dose and schedule for a median of 6 to 23 doses. The most common adverse reactions observed in patients receiving bevacizumab as a single agent or in combination with other anti-cancer therapies at a rate >10% were epistaxis, headache, hypertension, rhinitis, proteinuria, taste alteration, dry skin, hemorrhage, lacrimation disorder, back pain, and exfoliative dermatitis.

Across clinical studies, bevacizumab was discontinued in 8% to 22% of patients because of adverse reactions [see Clinical Studies (14)].

Metastatic Colorectal Cancer

In Combination with bolus-IFL

The safety of bevacizumab was evaluated in 392 patients who received at least one dose of bevacizumab in a double-blind, active-controlled study (AVF2107g), which compared bevacizumab (5 mg/kg every 2 weeks) with bolus-IFL to placebo with bolus-IFL in patients with mCRC [see Clinical Studies (14.1)]. Patients were randomized (1:1:1) to placebo with bolus-IFL, bevacizumab with bolus-IFL, or bevacizumab with fluorouracil and leucovorin. The demographics of the safety population were similar to the demographics of the efficacy population. All Grades 3 - 4 adverse reactions and selected Grades 1 - 2 adverse reactions (i.e., hypertension, proteinuria, thromboembolic events) were collected in the entire study population. Adverse reactions are presented in Table 2.

Table 2: Grades 3 - 4 Adverse Reactions Occurring at Higher Incidence (≥2%) in Patients Receiving Bevacizumabvs. Placebo in Study AVF2107g
Adverse Reactiona | Bevacizumabwith IFL (N=392) | Placebo with IFL (N=396)
Hematology
Leukopenia | 37% | 31%
Neutropenia | 21% | 14%
Gastrointestinal
Diarrhea | 34% | 25%
Abdominal pain | 8% | 5%
Constipation | 4% | 2%
Vascular
Hypertension | 12% | 2%
Deep vein thrombosis | 9% | 5%
Intra-abdominal thrombosis | 3% | 1%
Syncope | 3% | 1%
General
Asthenia | 10% | 7%
Pain | 8% | 5%
a NCI-CTC version 3

In Combination with FOLFOX4

The safety of bevacizumab was evaluated in 521 patients in an open-label, active-controlled study (E3200) in patients who were previously treated with irinotecan and fluorouracil for initial therapy for mCRC. Patients were randomized (1:1:1) to FOLFOX4, bevacizumab (10 mg/kg every 2 weeks prior to FOLFOX4 on Day 1) with FOLFOX4, or bevacizumab alone (10 mg/kg every 2 weeks). Bevacizumab was continued until disease progression or unacceptable toxicity.

The demographics of the safety population were similar to the demographics of the efficacy population.

Selected Grades 3 - 5 non-hematologic and Grades 4 to 5 hematologic occurring at a higher incidence (≥ 2%) in patients receiving bevacizumab with FOLFOX4 compared to FOLFOX4 alone were fatigue (19% vs. 13%), diarrhea (18% vs. 13%), sensory neuropathy (17% vs. 9%), nausea (12% vs. 5%), vomiting (11% vs. 4%), dehydration (10% vs. 5%), hypertension (9% vs. 2%), abdominal pain (8% vs. 5%), hemorrhage (5% vs. 1%), other neurological (5% vs. 3%), ileus (4% vs. 1%) and headache (3% vs. 0%). These data are likely to under-estimate the true adverse reaction rates due to the reporting mechanisms.

First-Line Non Squamous Non-Small Cell Lung Cancer

The safety of bevacizumab was evaluated as first-line treatment in 422 patients with unresectable NSCLC who received at least one dose of bevacizumab in an active-controlled, open-label, multicenter trial (E4599) [see Clinical Studies (14.3)]. Chemotherapy naïve patients with locally advanced, metastatic or recurrent non–squamous NSCLC were randomized (1:1) to receive six 21-day cycles of paclitaxel and carboplatin with or without bevacizumab (15 mg/kg every 3 weeks). After completion or upon discontinuation of chemotherapy, patients randomized to receive bevacizumab continued to receive bevacizumab alone until disease progression or until unacceptable toxicity. The trial excluded patients with predominant squamous histology (mixed cell type tumors only), CNS metastasis, gross hemoptysis (1/2 teaspoon or more of red blood), unstable angina, or receiving therapeutic anticoagulation. The demographics of the safety population were similar to the demographics of the efficacy population.

Only Grades 3 - 5 non-hematologic and Grades 4 - 5 hematologic adverse reactions were collected. Grades 3 - 5 non-hematologic and Grades 4 - 5 hematologic adverse reactions occurring at a higher incidence (≥ 2%) in patients receiving bevacizumab with paclitaxel and carboplatin compared with patients receiving chemotherapy alone were neutropenia (27% vs. 17%), fatigue (16% vs. 13%), hypertension (8% vs. 0.7%), infection without neutropenia (7% vs. 3%), venous thromboembolism (5% vs. 3%), febrile neutropenia (5% vs. 2%), pneumonitis/pulmonary infiltrates (5% vs. 3%), infection with Grade 3 or 4 neutropenia (4% vs. 2%), hyponatremia (4% vs. 1%), headache (3% vs. 1%) and proteinuria (3% vs. 0%).

Recurrent Glioblastoma

The safety of bevacizumab was evaluated in a multicenter, randomized, open-label study (EORTC 26101) in patients with recurrent GBM following radiotherapy and temozolomide of whom 278 patients received at least one dose of bevacizumab and are considered safety evaluable [see Clinical Studies (14.4)]. Patients were randomized (2:1) to receive bevacizumab (10 mg/kg every 2 weeks) with lomustine or lomustine alone until disease progression or unacceptable toxicity. The demographics of the safety population were similar to the demographics of the efficacy population. In the bevacizumab with lomustine arm, 22% of patients discontinued treatment due to adverse reactions compared with 10% of patients in the lomustine arm. In patients receiving bevacizumab with lomustine, the adverse reaction profile was similar to that observed in other approved indications.

Metastatic Renal Cell Carcinoma

The safety of bevacizumab was evaluated in 337 patients who received at least one dose of bevacizumab in a multicenter, double-blind study (BO17705) in patients with mRCC. Patients who had undergone a nephrectomy were randomized (1:1) to receive either bevacizumab (10 mg/kg every 2 weeks) or placebo with interferon alfa [see Clinical Studies (14.5)]. Patients were treated until disease progression or unacceptable toxicity. The demographics of the safety population were similar to the demographics of the efficacy population.

Grades 3 - 5 adverse reactions occurring at a higher incidence (>2%) were fatigue (13% vs. 8%), asthenia (10% vs. 7%), proteinuria (7% vs. 0%), hypertension (6% vs. 1%; including hypertension and hypertensive crisis), and hemorrhage (3% vs. 0.3%; including epistaxis, small intestinal hemorrhage, aneurysm ruptured, gastric ulcer hemorrhage, gingival bleeding, hemoptysis, hemorrhage intracranial, large intestinal hemorrhage, respiratory tract hemorrhage, and traumatic hematoma). Adverse reactions are presented in Table 3.

Table 3: Grades 1 - 5 Adverse Reactions Occurring at Higher Incidence (≥5%) of Patients Receiving Bevacizumabvs. Placebo with Interferon Alfa in Study BO17705
Adverse Reactiona | Bevacizumabwith Interferon Alfa (N=337) | Placebo with Interferon Alfa (N=304)
Metabolism and nutrition
Decreased appetite | 36% | 31%
Weight loss | 20% | 15%
General
Fatigue | 33% | 27%
Vascular
Hypertension | 28% | 9%
Respiratory, thoracic and mediastinal
Epistaxis | 27% | 4%
Dysphonia | 5% | 0%
Nervous system
Headache | 24% | 16%
Gastrointestinal
Diarrhea | 21% | 16%
Renal and urinary
Proteinuria | 20% | 3%
Musculoskeletal and connective tissue
Myalgia | 19% | 14%
Back pain | 12% | 6%
a NCI-CTC version 3

The following adverse reactions were reported at a 5-fold greater incidence in patients receiving bevacizumab with interferon-alfa compared to patients receiving placebo with interferon-alfa and not represented in Table 3: gingival bleeding (13 patients vs. 1 patient); rhinitis (9 vs. 0); blurred vision (8 vs. 0); gingivitis (8 vs. 1); gastroesophageal reflux disease (8 vs. 1); tinnitus (7 vs. 1); tooth abscess (7 vs. 0); mouth ulceration (6 vs. 0); acne (5 vs. 0); deafness (5 vs. 0); gastritis (5 vs. 0); gingival pain (5 vs. 0) and pulmonary embolism (5 vs. 1).

Persistent, Recurrent, or Metastatic Cervical Cancer

The safety of bevacizumab was evaluated in 218 patients who received at least one dose of bevacizumab in a multicenter study (GOG-0240) in patients with persistent, recurrent, or metastatic cervical cancer [see Clinical Studies (14.6)]. Patients were randomized (1:1:1:1) to receive paclitaxel and cisplatin with or without bevacizumab (15 mg/kg every 3 weeks), or paclitaxel and topotecan with or without bevacizumab (15 mg/kg every 3 weeks). The demographics of the safety population were similar to the demographics of the efficacy population.

Grades 3 - 4 adverse reactions occurring at a higher incidence (≥ 2%) in 218 patients receiving bevacizumab with chemotherapy compared to 222 patients receiving chemotherapy alone were abdominal pain (12% vs. 10%), hypertension (11% vs. 0.5%), thrombosis (8% vs. 3%), diarrhea (6% vs. 3%), anal fistula (4% vs. 0%), proctalgia (3% vs. 0%), urinary tract infection (8% vs. 6%), cellulitis (3% vs. 0.5%), fatigue (14% vs. 10%), hypokalemia (7% vs. 4%), hyponatremia (4% vs. 1%), dehydration (4% vs. 0.5%), neutropenia (8% vs. 4%), lymphopenia (6% vs. 3%), back pain (6% vs. 3%), and pelvic pain (6% vs. 1%). Adverse reactions are presented in Table 4.

Table 4: Grades 1 - 4 Adverse Reactions Occurring at Higher Incidence (≥ 5%) in Patients Receiving Bevacizumabwith Chemotherapy vs. Chemotherapy Alone in Study GOG-0240
Adverse Reactiona | Bevacizumabwith Chemotherapy (N=218) | Chemotherapy (N=222)
General
Fatigue | 80% | 75%
Peripheral edema | 15% | 22%
Metabolism and nutrition
Decreased appetite | 34% | 26%
Hyperglycemia | 26% | 19%
Hypomagnesemia | 24% | 15%
Weight loss | 21% | 7%
Hyponatremia | 19% | 10%
Hypoalbuminemia | 16% | 11%
Vascular
Hypertension | 29% | 6%
Thrombosis | 10% | 3%
Infections
Urinary tract infection | 22% | 14%
Infection | 10% | 5%
Nervous system
Headache | 22% | 13%
Dysarthria | 8% | 1%
Psychiatric
Anxiety | 17% | 10%
Respiratory, thoracic and mediastinal
Epistaxis | 17% | 1%
Renal and urinary
Increased blood creatinine | 16% | 10%
Proteinuria | 10% | 3%
Gastrointestinal
Stomatitis | 15% | 10%
Proctalgia | 6% | 1%
Anal fistula | 6% | 0%
Reproductive system and breast
Pelvic pain | 14% | 8%
Hematology
Neutropenia | 12% | 6%
Lymphopenia | 12% | 5%
a NCI-CTC version 3

Epithelial Ovarian, Fallopian Tube or Primary Peritoneal Cancer

Platinum-Resistant Recurrent Epithelial Ovarian, Fallopian Tube, or Primary Peritoneal Cancer

The safety of bevacizumab was evaluated in 179 patients who received at least one dose of bevacizumab in a multicenter, open-label study (MO22224) in which patients were randomized (1:1) to bevacizumab with chemotherapy or chemotherapy alone in patients with platinum resistant, recurrent epithelial ovarian, fallopian tube, or primary peritoneal cancer that recurred within < 6 months from the most recent platinum based therapy [see Clinical Studies (14.8)]. Patients were randomized to receive bevacizumab 10 mg/kg every 2 weeks or 15 mg/kg every 3 weeks. Patients had received no more than 2 prior chemotherapy regimens. The trial excluded patients with evidence of recto-sigmoid involvement by pelvic examination or bowel involvement on CT scan or clinical symptoms of bowel obstruction. Patients were treated until disease progression or unacceptable toxicity. Forty percent of patients on the chemotherapy alone arm received bevacizumab alone upon progression. The demographics of the safety population were similar to the demographics of the efficacy population.

Grades 3 - 4 adverse reactions occurring at a higher incidence (≥ 2%) in 179 patients receiving bevacizumab with chemotherapy compared to 181 patients receiving chemotherapy alone were hypertension (6.7% vs. 1.1%) and palmar-plantar erythrodysaesthesia syndrome (4.5% vs. 1.7%). Adverse reactions are presented in Table 6.

Table 6: Grades 2 - 4 Adverse Reactions Occurring at Higher Incidence (≥ 5%) in Patients Receiving Bevacizumabwith Chemotherapy vs. Chemotherapy Alone in Study MO22224
Adverse Reactiona | Bevacizumabwith Chemotherapy (N=179) | Chemotherapy (N=181)
Hematology
Neutropenia | 31% | 25%
Vascular
Hypertension | 19% | 6%
Nervous system
Peripheral sensory neuropathy | 18% | 7%
General
Mucosal inflammation | 13% | 6%
Renal and urinary
Proteinuria | 12% | 0.6%
Skin and subcutaneous tissue
Palmar-plantar erythrodysaesthesia | 11% | 5%
Infections
Infection | 11% | 4%
Respiratory, thoracic and mediastinal
Epistaxis | 5% | 0%
a NCI-CTC version 3

6.2 Immunogenicity

As with all therapeutic proteins, there is a potential for immunogenicity. The detection of antibody formation is highly dependent on the sensitivity and the specificity of the assay. Additionally, the observed incidence of antibody (including neutralizing antibody) positivity in an assay may be influenced by several factors, including assay methodology, sample handling, timing of sample collection, concomitant medications, and underlying disease. For these reasons, comparison of the incidence of antibodies in the studies described below with the incidence of antibodies in other studies or to other bevacizumab products may be misleading.

In clinical studies for adjuvant treatment of a solid tumor, 0.6% (14/2233) of patients tested positive for treatment-emergent anti-bevacizumab antibodies as detected by an electrochemiluminescent (ECL) based assay. Among these 14 patients, three tested positive for neutralizing antibodies against bevacizumab using an enzyme-linked immunosorbent assay (ELISA). The clinical significance of these anti-bevacizumab antibodies is not known.

6.3 Postmarketing Experience

The following adverse reactions have been identified during postapproval use of bevacizumab products. Because these reactions are reported voluntarily from a population of uncertain size, it is not always possible to reliably estimate their frequency or establish a causal relationship to drug exposure.

General: Polyserositis

Cardiovascular: Pulmonary hypertension, Mesenteric venous occlusion

Gastrointestinal: Gastrointestinal ulcer, Intestinal necrosis, Anastomotic ulceration

Hemic and lymphatic: Pancytopenia

Hepatobiliary disorders: Gallbladder perforation

Musculoskeletal and Connective Tissue Disorders: Osteonecrosis of the jaw

Renal: Renal thrombotic microangiopathy (manifested as severe proteinuria)

Respiratory: Nasal septum perforation

Vascular: Arterial (including aortic) aneurysms, dissections, and rupture

7 DRUG INTERACTIONS

Effects of Alymsyson Other Drugs

No clinically meaningful effect on the pharmacokinetics of irinotecan or its active metabolite SN38, interferon alfa, carboplatin or paclitaxel was observed when bevacizumab was administered in combination with these drugs; however, 3 of the 8 patients receiving bevacizumab with paclitaxel and carboplatin had lower paclitaxel exposure after four cycles of treatment (at Day 63) than those at Day 0, while patients receiving paclitaxel and carboplatin alone had a greater paclitaxel exposure at Day 63 than at Day 0.

8 USE IN SPECIFIC POPULATIONS

8.1 Pregnancy

Risk Summary

Based on findings from animal studies and their mechanism of action [see Clinical Pharmacology (12.1)], bevacizumab products may cause fetal harm in pregnant women. Limited postmarketing reports describe cases of fetal malformations with use of bevacizumab products in pregnancy; however, these reports are insufficient to determine drug-associated risks. In animal reproduction studies, intravenous administration of bevacizumab to pregnant rabbits every 3 days during organogenesis at doses approximately 1 to 10 times the clinical dose of 10 mg/kg produced fetal resorptions, decreased maternal and fetal weight gain and multiple congenital malformations including corneal opacities and abnormal ossification of the skull and skeleton including limb and phalangeal defects (see Data). Furthermore, animal models link angiogenesis and VEGF and VEGFR2 to critical aspects of female reproduction, embryofetal development, and postnatal development. Advise pregnant women of the potential risk to a fetus.

In the U.S. general population, the estimated background risk of major birth defects and miscarriage in clinically recognized pregnancies is 2% to 4% and 15% to 20%, respectively.

Data

Animal Data

Pregnant rabbits dosed with 10 mg/kg to 100 mg/kg bevacizumab (approximately 1 to 10 times the clinical dose of 10 mg/kg) every three days during the period of organogenesis (gestation day 6 to 18) exhibited decreases in maternal and fetal body weights and increased number of fetal resorptions. There were dose-related increases in the number of litters containing fetuses with any type of malformation (42% for the 0 mg/kg dose, 76% for the 30 mg/kg dose, and 95% for the 100 mg/kg dose) or fetal alterations (9% for the 0 mg/kg dose, 15% for the 30 mg/kg dose, and 61% for the 100 mg/kg dose). Skeletal deformities were observed at all dose levels, with some abnormalities including meningocele observed only at the 100 mg/kg dose level. Teratogenic effects included: reduced or irregular ossification in the skull, jaw, spine, ribs, tibia and bones of the paws; fontanel, rib and hindlimb deformities; corneal opacity; and absent hindlimb phalanges.

8.2 Lactation

Risk Summary

No data are available regarding the presence of bevacizumab products in human milk, the effects on the breast fed infant, or the effects on milk production. Human IgG is present in human milk, but published data suggest that breast milk antibodies do not enter the neonatal and infant circulation in substantial amounts. Because of the potential for serious adverse reactions in breastfed infants from bevacizumab products, advise women not to breastfeed during treatment with Alymsys and for 6 months after the last dose.

8.3 Females and Males of Reproductive Potential

Contraception

Females

Bevacizumab products may cause fetal harm when administered to a pregnant woman [see Use in Specific Populations (8.1)]. Advise females of reproductive potential to use effective contraception during treatment with Alymsys and for 6 months after the last dose.

Infertility

Females

Bevacizumab products increase the risk of ovarian failure and may impair fertility. Inform females of reproductive potential of the risk of ovarian failure prior to the first-dose of Alymsys. Long-term effects of bevacizumab products on fertility are not known.

In a clinical study of 179 premenopausal women randomized to receive chemotherapy with or without bevacizumab, the incidence of ovarian failure was higher in patients who received bevacizumab with chemotherapy (34%) compared to patients who received chemotherapy alone (2%). After discontinuing bevacizumab with chemotherapy, recovery of ovarian function occurred in 22% of these patients [see Warnings and Precautions (5.11), Adverse Reactions (6.1)].

8.4 Pediatric Use

The safety and effectiveness of bevacizumab products in pediatric patients have not been established.

In published literature reports, cases of non-mandibular osteonecrosis have been observed in patients under the age of 18 years who received bevacizumab. Bevacizumab products are not approved for use in patients under the age of 18 years.

Antitumor activity was not observed among eight pediatric patients with relapsed GBM who received bevacizumab and irinotecan. Addition of bevacizumab to standard of care did not result in improved event-free survival in pediatric patients enrolled in two randomized clinical studies, one in high grade glioma (n= 121) and one in metastatic rhabdomyosarcoma or non-rhabdomyosarcoma soft tissue sarcoma (n= 154).

Based on the population pharmacokinetics analysis of data from 152 pediatric and young adult patients with cancer (7 months to 21 years of age), bevacizumab clearance normalized by body weight in pediatrics was comparable to that in adults.

Juvenile Animal Toxicity Data

Juvenile cynomolgus monkeys with open growth plates exhibited physeal dysplasia following 4 to 26 weeks exposure at 0.4 to 20 times the recommended human dose (based on mg/kg and exposure). The incidence and severity of physeal dysplasia were dose-related and were partially reversible upon cessation of treatment.

8.5 Geriatric Use

In an exploratory pooled analysis of 1,745 patients from five randomized, controlled studies, 35% of patients were ≥65 years old. The overall incidence of ATE was increased in all patients receiving bevacizumab with chemotherapy as compared to those receiving chemotherapy alone, regardless of age; however, the increase in the incidence of ATE was greater in patients ≥65 years (8% vs. 3%) as compared to patients <65 years (2% vs. 1%) [see Warnings and Precautions (5.4)].

11 DESCRIPTION

Bevacizumab-maly is a vascular endothelial growth factor inhibitor. Bevacizumab-maly is a recombinant humanized monoclonal IgG1 antibody that contains human framework regions and murine complementarity-determining regions. Bevacizumab-maly has an approximate molecular weight of 149 kDa. Bevacizumab-maly is produced in a mammalian cell (Chinese Hamster Ovary) expression system.

Alymsys (bevacizumab-maly) injection is a sterile, preservative-free, clear to slightly opalescent, colorless to pale brown solution in a single-dose vial for intravenous use. Alymsys contains bevacizumab-maly at a concentration of 25 mg/mL in either a 100 mg/4 mL or 400 mg/16 mL single-dose vial.

Each mL of solution contains 25 mg bevacizumab-maly, α,α-trehalose dihydrate (60 mg), polysorbate 20 (0.4 mg), sodium phosphate dibasic, anhydrous (1.2 mg), sodium phosphate monobasic, monohydrate (5.8 mg), and Water for Injection, USP. The pH is 6.2.

12 CLINICAL PHARMACOLOGY

12.1 Mechanism of Action

Bevacizumab products bind VEGF and prevent the interaction of VEGF to its receptors (Flt-1 and KDR) on the surface of endothelial cells. The interaction of VEGF with its receptors leads to endothelial cell proliferation and new blood vessel formation in in vitro models of angiogenesis. Administration of bevacizumab to xenotransplant models of colon cancer in nude (athymic) mice caused reduction of microvascular growth and inhibition of metastatic disease progression.

12.3 Pharmacokinetics

The pharmacokinetic profile of bevacizumab was assessed using an assay that measures total serum bevacizumab concentrations (i.e., the assay did not distinguish between free bevacizumab and bevacizumab bound to VEGF ligand). Based on a population pharmacokinetic analysis of 491 patients who received 1 to 20 mg/kg of bevacizumab every week, every 2 weeks, or every 3 weeks, bevacizumab pharmacokinetics are linear and the predicted time to reach more than 90% of steady state concentration is 84 days. The accumulation ratio following a dose of 10 mg/kg of bevacizumab once every 2 weeks is 2.8.

Population simulations of bevacizumab exposures provide a median trough concentration of 80.3 mcg/mL on Day 84 (10th, 90th percentile: 45, 128) following a dose of 5 mg/kg once every two weeks.

Distribution

The mean (% coefficient of variation [CV%]) central volume of distribution is 2.9 (22%) L.

Elimination

The mean (CV%) clearance is 0.23 (33) L/day. The estimated half-life is 20 days (11 to 50 days).

Specific Populations

The clearance of bevacizumab varied by body weight, sex, and tumor burden. After correcting for body weight, males had a higher bevacizumab clearance (0.26 L/day vs. 0.21 L/day) and a larger central volume of distribution (3.2 L vs. 2.7 L) than females. Patients with higher tumor burden (at or above median value of tumor surface area) had a higher bevacizumab clearance (0.25 L/day vs. 0.20 L/day) than patients with tumor burdens below the median. In Study AVF2107g, there was no evidence of lesser efficacy (hazard ratio for overall survival) in males or patients with higher tumor burden treated with bevacizumab as compared to females and patients with low tumor burden.

13 NONCLINICAL TOXICOLOGY

13.1 Carcinogenesis and Mutagenesis and Impairment of Fertility

No studies have been conducted to assess potential of bevacizumab products for carcinogenicity or mutagenicity.

Bevacizumab products may impair fertility. Female cynomolgus monkeys treated with 0.4 to 20 times the recommended human dose of bevacizumab exhibited arrested follicular development or absent corpora lutea, as well as dose-related decreases in ovarian and uterine weights, endometrial proliferation, and the number of menstrual cycles. Following a 4- or 12-week recovery period, there was a trend suggestive of reversibility. After the 12-week recovery period, follicular maturation arrest was no longer observed, but ovarian weights were still moderately decreased. Reduced endometrial proliferation was no longer observed at the 12-week recovery time point; however, decreased uterine weight, absent corpora lutea, and reduced number of menstrual cycles remained evident.

13.2 Animal Toxicology and/or Pharmacology

Rabbits dosed with bevacizumab exhibited reduced wound healing capacity. Using full-thickness skin incision and partial thickness circular dermal wound models, bevacizumab dosing resulted in reductions in wound tensile strength, decreased granulation and re-epithelialization, and delayed time to wound closure.

14 CLINICAL STUDIES

14.1 Metastatic Colorectal Cancer

Study AVF2107g

The safety and efficacy of bevacizumab was evaluated in a double-blind, active-controlled study [AVF2107g (NCT00109070)] in 923 patients with previously untreated mCRC who were randomized (1:1:1) to placebo with bolus-IFL (irinotecan 125 mg/m^2, fluorouracil 500 mg/m^2, and leucovorin 20 mg/m^2 given once weekly for 4 weeks every 6 weeks), bevacizumab (5 mg/kg every 2 weeks) with bolus-IFL, or bevacizumab (5 mg/kg every 2 weeks) with fluorouracil and leucovorin. Enrollment to the bevacizumab with fluorouracil and leucovorin arm was discontinued after enrollment of 110 patients in accordance with the protocol-specified adaptive design. Bevacizumab was continued until disease progression or unacceptable toxicity or for a maximum of 96 weeks. The main outcome measure was overall survival (OS).

The median age was 60 years; 60% were male, 79% were White, 57% had an ECOG performance status of 0, 21% had a rectal primary and 28% received prior adjuvant chemotherapy. The dominant site of disease was extra-abdominal in 56% of patients and was the liver in 38% of patients.

The addition of bevacizumab improved survival across subgroups defined by age (< 65 years, ≥65 years) and sex. Results are presented in Table 6 and Figure 1.

Table 6: Efficacy Results in Study AVF2107g
Efficacy Parameter | Bevacizumab with bolus-IFL (N=402) | Placebo with bolus-IFL (N=411)
Overall Survival
Median, in months | 20.3 | 15.6
Hazard ratio (95% CI) | 0.66 (0.54, 0.81)
p-valuea | < 0.001
Progression-Free Survival
Median, in months | 10.6 | 6.2
Hazard ratio (95% CI) | 0.54 (0.45, 0.66)
p-valuea | < 0.001
Overall Response Rate
Rate (%) | 45% | 35%
p-valueb | < 0.01
Duration of Response
Median, in months | 10.4 | 7.1
a by stratified log-rank test.
b by χ^2 test

Figure 1: Kaplan-Meier Curves for Duration of Survival in Metastatic Colorectal Cancer in Study AVF2107g

Among the 110 patients randomized to bevacizumab with fluorouracil and leucovorin, median OS was 18.3 months, median progression-free survival (PFS) was 8.8 months, overall response rate (ORR) was 39%, and median duration of response was 8.5 months.

Study E3200

The safety and efficacy of bevacizumab were evaluated in a randomized, open-label, active-controlled study [E3200 (NCT00025337)] in 829 patients who were previously treated with irinotecan and fluorouracil for initial therapy for metastatic disease or as adjuvant therapy. Patients were randomized (1:1:1) to FOLFOX4 (Day 1: oxaliplatin 85 mg/m^2 and leucovorin 200 mg/m^2 concurrently, then fluorouracil 400 mg/m^2 bolus followed by 600 mg/m^2 continuously; Day 2: leucovorin 200 mg/m^2, then fluorouracil 400 mg/m^2 bolus followed by 600 mg/m^2 continuously; every 2 weeks), bevacizumab (10 mg/kg every 2 weeks prior to FOLFOX4 on Day 1) with FOLFOX4, or bevacizumab alone (10 mg/kg every 2 weeks). Bevacizumab was continued until disease progression or unacceptable toxicity. The main outcome measure was OS.

The bevacizumab alone arm was closed to accrual after enrollment of 244 of the planned 290 patients following a planned interim analysis by the data monitoring committee based on evidence of decreased survival compared to FOLFOX4 alone.

The median age was 61 years; 60% were male, 87% were White, 49% had an ECOG performance status of 0, 26% received prior radiation therapy, and 80% received prior adjuvant chemotherapy, 99% received prior irinotecan with or without fluorouracil for metastatic disease, and 1% received prior irinotecan and fluorouracil as adjuvant therapy.

The addition of bevacizumab to FOLFOX4 resulted in significantly longer survival as compared to FOLFOX4 alone; median OS was 13.0 months vs. 10.8 months [hazard ratio (HR) 0.75 (95% CI: 0.63, 0.89), p-value of 0.001 stratified log-rank test] with clinical benefit seen in subgroups defined by age (< 65 years, ≥65 years) and sex. PFS and ORR based on investigator assessment were higher in patients receiving bevacizumab with FOLFOX4.

Study TRC-0301

The activity of bevacizumab with fluorouracil (as bolus or infusion) and leucovorin was evaluated in a single arm study [TRC-0301 (NCT00066846)] enrolling 339 patients with mCRC with disease progression following both irinotecan- and oxaliplatin-based chemotherapy. Seventy-three percent of patients received concurrent bolus fluorouracil and leucovorin. One objective partial response was verified in the first 100 evaluable patients for an ORR of 1% (95% CI: 0%, 5.5%).

Study ML18147

The safety and efficacy of bevacizumab were evaluated in a prospective, randomized, open-label, multinational, controlled study [ML18147 (NCT00700102)] in 820 patients with histologically confirmed mCRC who had progressed on a first-line bevacizumab-containing regimen. Patients were excluded if they progressed within 3 months of initiating first-line chemotherapy and if they received bevacizumab for less than 3 consecutive months in the first-line setting. Patients were randomized (1:1) within 3 months after discontinuing bevacizumab as first-line treatment to receive fluoropyrimidine-irinotecan- or fluoropyrimidine-oxaliplatin-based chemotherapy with or without bevacizumab (5 mg/kg every 2 weeks or 7.5 mg/kg every 3 weeks). The choice of second-line treatment was contingent upon first-line chemotherapy. Second-line treatment was administered until progressive disease or unacceptable toxicity. The main outcome measure was OS. A secondary outcome measure was ORR.

The median age was 63 years (21 to 84 years); 64% were male, 52% had an ECOG performance status of 1, 44% had an ECOG performance status of 0, 58% received irinotecan-based therapy as first-line treatment, 55% progressed on first-line treatment within 9 months, and 77% received their last dose of bevacizumab as first-line treatment within 42 days of being randomized. Second-line chemotherapy regimens were generally balanced between each arm.

The addition of bevacizumab to fluoropyrimidine-based chemotherapy resulted in a statistically significant prolongation of OS and PFS. There was no significant difference in ORR. Results are presented in Table 7 and Figure 2.

Table 7: Efficacy Results in Study ML18147
Efficacy Parameter | Bevacizumab with Chemotherapy (N=409) | Chemotherapy (N=411)
Overall Survivala
Median, in months | 11.2 | 9.8
Hazard ratio (95% CI) | 0.81 (0.69, 0.94)
Progression-Free Survivalb
Median, in months | 5.7 | 4.0
Hazard ratio (95% CI) | 0.68 (0.59, 0.78)
a p=0.0057 by unstratified log-rank test.
b p-value < 0.0001 by unstratified log-rank test.

Figure 2: Kaplan-Meier Curves for Duration of Survival in Metastatic Colorectal Cancer in Study ML18147

14.2 Lack of Efficacy in Adjuvant Treatment of Colon Cancer

Lack of efficacy of bevacizumab as an adjunct to standard chemotherapy for the adjuvant treatment of colon cancer was determined in two randomized, open-label, multicenter clinical studies.

The first study [BO17920 (NCT00112918)] was conducted in 3451 patients with high-risk stage II and III colon cancer, who had undergone surgery for colon cancer with curative intent. Patients were randomized to receive bevacizumab at a dose equivalent to 2.5 mg/kg/week on either a 2-weekly schedule with FOLFOX4 (N=1155) or on a 3-weekly schedule with XELOX (N=1145) or FOLFOX4 alone (N=1151). The main outcome measure was disease free survival (DFS) in patients with stage III colon cancer.

The median age was 58 years; 54% were male, 84% were White and 29% were ≥ 65 years. Eighty-three percent had stage III disease.

The addition of bevacizumab to chemotherapy did not improve DFS. As compared to FOLFOX4 alone, the proportion of stage III patients with disease recurrence or with death due to disease progression were numerically higher for patients receiving bevacizumab with FOLFOX4 or with XELOX. The hazard ratios for DFS were 1.17 (95% CI: 0.98,1.39) for bevacizumab with FOLFOX4 versus FOLFOX4 alone and 1.07 (95% CI: 0.90, 1.28) for bevacizumab with XELOX versus FOLFOX4 alone. The hazard ratios for OS were 1.31 (95% CI: 1.03, 1.67) and 1.27 (95% CI: 1, 1.62) for the comparison of bevacizumab with FOLFOX4 versus FOLFOX4 alone and bevacizumab with XELOX versus FOLFOX4 alone, respectively. Similar lack of efficacy for DFS was observed in the bevacizumab-containing arms compared to FOLFOX4 alone in the high-risk stage II cohort.

In a second study [NSABP-C-08 (NCT00096278)], patients with stage II and III colon cancer who had undergone surgery with curative intent, were randomized to receive either bevacizumab administered at a dose equivalent to 2.5 mg/kg/week with mFOLFOX6 (N=1354) or mFOLFOX6 alone (N=1356). The median age was 57 years, 50% were male and 87% White. Seventy-five percent had stage III disease. The main outcome was DFS among stage III patients. The HR for DFS was 0.92 (95% CI: 0.77, 1.10). OS was not significantly improved with the addition of bevacizumab to mFOLFOX6 [HR 0.96 (95% CI: 0.75,1.22)].

14.3 First-Line Non–Squamous Non–Small Cell Lung Cancer

Study E4599

The safety and efficacy of bevacizumab as first-line treatment of patients with locally advanced, metastatic, or recurrent non–squamous NSCLC was studied in a single, large, randomized, active-controlled, open-label, multicenter study [E4599 (NCT00021060)]. A total of 878 chemotherapy-naïve patients with locally advanced, metastatic or recurrent non–squamous NSCLC were randomized (1:1) to receive six 21-day cycles of paclitaxel (200 mg/m^2) and carboplatin (AUC 6) with or without bevacizumab 15 mg/kg. After completing or discontinuing chemotherapy, patients randomized to receive bevacizumab continued to receive bevacizumab alone until disease progression or until unacceptable toxicity. The trial excluded patients with predominant squamous histology (mixed cell type tumors only), CNS metastasis, gross hemoptysis (1/2 teaspoon or more of red blood), unstable angina, or receiving therapeutic anticoagulation. The main outcome measure was duration of survival.

The median age was 63 years; 54% were male, 43% were ≥65 years, and 28% had ≥5% weight loss at study entry. Eleven percent had recurrent disease. Of the 89% with newly diagnosed NSCLC, 12% had Stage IIIB with malignant pleural effusion and 76% had Stage IV disease.

OS was statistically significantly longer for patients receiving bevacizumab with paclitaxel and carboplatin compared with those receiving chemotherapy alone. Median OS was 12.3 months vs. 10.3 months [HR 0.80 (95% CI: 0.68, 0.94), final p-value of 0.013, stratified log-rank test]. Based on investigator assessment which was not independently verified, patients were reported to have longer PFS with bevacizumab with paclitaxel and carboplatin compared to chemotherapy alone. Results are presented in Figure 3.

Figure 3: Kaplan-Meier Curves for Duration of Survival in First-Line Non-Squamous Non-Small Cell Lung Cancer in Study E4599

In an exploratory analysis across patient subgroups, the impact of bevacizumab on OS was less robust in the following subgroups: women [HR 0.99 (95% CI: 0.79, 1.25)], patients ≥65 years [HR 0.91 (95% CI: 0.72, 1.14)] and patients with ≥5% weight loss at study entry [HR 0.96 (95% CI: 0.73, 1.26)].

Study BO17704

The safety and efficacy of bevacizumab in patients with locally advanced, metastatic or recurrent non-squamous NSCLC, who had not received prior chemotherapy was studied in another randomized, double-blind, placebo-controlled study [BO17704 (NCT00806923)]. A total of 1,043 patients were randomized (1:1:1) to receive cisplatin and gemcitabine with placebo, bevacizumab 7.5 mg/kg or bevacizumab 15 mg/kg. The main outcome measure was PFS. Secondary outcome measure was OS.

The median age was 58 years; 36% were female and 29% were ≥ 65 years. Eight percent had recurrent disease and 77% had Stage IV disease.

PFS was significantly higher in both bevacizumab-containing arms compared to the placebo arm [HR 0.75 (95% CI: 0.62, 0.91), p-value of 0.0026 for bevacizumab 7.5 mg/kg and HR 0.82 (95% CI: 0.68; 0.98), p-value of 0.0301 for bevacizumab 15 mg/kg]. The addition of bevacizumab to cisplatin and gemcitabine failed to demonstrate an improvement in the duration of OS [HR 0.93 (95% CI: 0.78; 1.11), p-value of 0.420 for bevacizumab 7.5 mg/kg and HR 1.03 (95%

CI: 0.86, 1.23), p-value of 0.761 for bevacizumab 15 mg/kg].

14.4 Recurrent Glioblastoma

Study EORTC 26101

The safety and efficacy of bevacizumab were evaluated in a multicenter, randomized (2:1), open-label study in patients with recurrent GBM (EORTC 26101, NCT01290939). Patients with first progression following radiotherapy and temozolomide were randomized (2:1) to receive bevacizumab (10 mg/kg every 2 weeks) with lomustine (90 mg/m^2 every 6 weeks) or lomustine (110 mg/m^2 every 6 weeks) alone until disease progression or unacceptable toxicity. Randomization was stratified by World Health Organization performance status (0 vs. >0), steroid use (yes vs. no), largest tumor diameter (≤ 40 vs. > 40 mm), and institution. The main outcome measure was OS. Secondary outcome measures were investigator-assessed PFS and ORR per the modified Response Assessment in Neuro-oncology (RANO) criteria, health related quality of life (HRQoL), cognitive function, and corticosteroid use.

A total of 432 patients were randomized to receive lomustine alone (N=149) or bevacizumab with lomustine (N=283). The median age was 57 years; 24.8% of patients were ≥ 65 years. The majority of patients with were male (61%); 66% had a WHO performance status score > 0; and in 56% the largest tumor diameter was ≤ 40 mm. Approximately 33% of patients randomized to receive lomustine received bevacizumab following documented progression.

No difference in OS (HR 0.91, p -value of 0.4578) was observed between arms; therefore, all secondary outcome measures are descriptive only. PFS was longer in the bevacizumab with lomustine arm [HR 0.52 (95% CI: 0.41, 0.64)] with a median PFS of 4.2 months in the bevacizumab with lomustine arm and 1.5 months in the lomustine arm. Among the 50% of patients receiving corticosteroids at the time of randomization, a higher percentage of patients in the bevacizumab with lomustine arm discontinued corticosteroids (23% vs. 12%).

Study AVF3708g and Study NCI 06-C-0064E

The efficacy and safety of bevacizumab 10 mg/kg every 2 weeks in patients with previously treated GBM were evaluated in one single arm single center study (NCI 06-C-0064E) and a randomized noncomparative multicenter study [AVF3708g (NCT00345163)]. Response rates in both studies were evaluated based on modified WHO criteria that considered corticosteroid use. In AVF3708g, the response rate was 25.9% (95% CI: 17%, 36.1%) with a median duration of response of 4.2 months (95% CI: 3, 5.7). In Study NCI 06-C-0064E, the response rate was 19.6% (95% CI: 10.9%, 31.3%) with a median duration of response of 3.9 months (95% CI: 2.4, 17.4).

14.5 Metastatic Renal Cell Carcinoma

Study BO17705

The safety and efficacy of bevacizumab were evaluated in patients with treatment-naïve mRCC in a multicenter, randomized, double-blind, international study [BO17705 (NCT00738530)] comparing interferon alfa and bevacizumab versus interferon alfa and placebo. A total of 649 patients who had undergone a nephrectomy were randomized (1:1) to receive either bevacizumab (10 mg/kg every 2 weeks; N = 327) or placebo (every 2 weeks; N = 322) with interferon alfa (9 MIU subcutaneously three times weekly for a maximum of 52 weeks). Patients were treated until disease progression or unacceptable toxicity. The main outcome measure was investigator-assessed PFS. Secondary outcome measures were ORR and OS.

The median age was 60 years (18 to 82 years); 70% were male and 96% were White. The study population was characterized by Motzer scores as follows: 28% favorable (0), 56% intermediate (1-2), 8% poor (3 to 5), and 7% missing.

PFS was statistically significantly prolonged among patients receiving bevacizumab compared to placebo; median PFS was 10.2 months vs. 5.4 months [HR 0.60 (95% CI: 0.49, 0.72), p-value < 0.0001, stratified log-rank test]. Among the 595 patients with measurable disease, ORR was also significantly higher (30% vs. 12%, p-value < 0.0001, stratified CMH test). There was no improvement in OS based on the final analysis conducted after 444 deaths, with a median OS of 23 months in the patients receiving bevacizumab with interferon alfa and 21 months in patients receiving interferon alone [HR 0.86, (95% CI: 0.72, 1.04)]. Results are presented in Figure 4.

Figure 4: Kaplan-Meier Curves for Progression-Free Survival in Metastatic Renal Cell Carcinoma in

Study BO17705

14.6 Persistent, Recurrent, or Metastatic Cervical Cancer

Study GOG-0240

The safety and efficacy of bevacizumab were evaluated in patients with persistent, recurrent, or metastatic cervical cancer in a randomized, four-arm, multicenter study comparing bevacizumab with chemotherapy versus chemotherapy alone [GOG-0240 (NCT00803062)]. A total of 452 patients were randomized (1:1:1:1) to receive paclitaxel and cisplatin with or without bevacizumab, or paclitaxel and topotecan with or without bevacizumab.

The dosing regimens for bevacizumab, paclitaxel, cisplatin and topotecan were as follows:

- Day 1: Paclitaxel 135 mg/m^2 over 24 hours, Day 2: cisplatin 50 mg/m^2 with bevacizumab;
- Day 1: Paclitaxel 175 mg/m^2 over 3 hours, Day 2: cisplatin 50 mg/m^2 with bevacizumab;
- Day 1: Paclitaxel 175 mg/m^2 over 3 hours with cisplatin 50 mg/m^2 with bevacizumab;
- Day 1: Paclitaxel 175 mg/m^2 over 3 hours with bevacizumab, Days 1 to 3: topotecan IV 0.75 mg/m^2 over 30 minutes

Patients were treated until disease progression or unacceptable adverse reactions. The main outcome measure was OS. Secondary outcome measures included ORR.

The median age was 48 years (20 to 85 years). Of the 452 patients randomized at baseline, 78% of patients were White, 80% had received prior radiation, 74% had received prior chemotherapy concurrent with radiation, and 32% had a platinum-free interval of less than 6 months. Patients had a GOG performance status of 0 (58%) or 1 (42%). Demographic and disease characteristics were balanced across arms.

Results are presented in Figure 5 and Table 8.

Figure 5: Kaplan-Meier Curves for Overall Survival in Persistent, Recurrent, or Metastatic Cervical Cancer in Study GOG-0240

Table 8: Efficacy Results in Study GOG-0240
Efficacy Parameter | Bevacizumab with Chemotherapy (N=227) | Chemotherapy (N=225)
Overall Survival
Median, in monthsa | 16.8 | 12.9
Hazard ratio (95% CI) | 0.74 (0.58, 0.94)
p-valueb | 0.0132
a Kaplan-Meier estimates.
b log-rank test (stratified).

The ORR was higher in patients who received bevacizumab with chemotherapy [45% (95% CI: 39, 52)] compared to patients who received chemotherapy alone [34% (95% CI: 28,40)].

Table 9: Efficacy Results in Study GOG-0240
Efficacy Parameter | Topotecan and Paclitaxel with or without Bevacizumab (N=223) | Cisplatin and Paclitaxel with or without Bevacizumab (N=229)
Overall Survival
Median, in monthsa | 13.3 | 15.5
Hazard ratio (95% CI) | 1.15 (0.91, 1.46)
p-value | 0.23
a Kaplan-Meier estimates.

The HR for OS with bevacizumab with cisplatin and paclitaxel as compared to cisplatin and paclitaxel alone was 0.72 (95% CI: 0.51,1.02). The HR for OS with bevacizumab with topotecan and paclitaxel as compared to topotecan and paclitaxel alone was 0.76 (95% CI: 0.55, 1.06).

14.7 Platinum-Resistant Recurrent Epithelial Ovarian, Fallopian Tube, or Primary Peritoneal Cancer

Study MO22224

The safety and efficacy of bevacizumab were evaluated in a multicenter, open-label, randomized study [MO22224 (NCT00976911)] comparing bevacizumab with chemotherapy versus chemotherapy alone in patients with platinum-resistant, recurrent epithelial ovarian, fallopian tube, or primary peritoneal cancer that recurred within <6 months from the most recent platinum-based therapy (N=361). Patients had received no more than 2 prior chemotherapy regimens. Patients received one of the following chemotherapy regimens at the discretion of the investigator: paclitaxel (80 mg/m^2 on days 1, 8, 15 and 22 every 4 weeks; pegylated liposomal doxorubicin 40 mg/m^2 on day 1 every 4 weeks; or topotecan 4 mg/m^2 on days 1, 8 and 15 every 4 weeks or 1.25 mg/m^2 on days 1 - 5 every 3 weeks). Patients were treated until disease progression, unacceptable toxicity, or withdrawal. Forty percent of patients on the chemotherapy alone arm received bevacizumab alone upon progression. The main outcome measure was investigator-assessed PFS. Secondary outcome measures were ORR and OS.

The median age was 61 years (25 to 84 years) and 37% of patients were ≥65 years. Seventy-nine percent had measurable disease at baseline, 87% had baseline CA-125 levels ≥2 times ULN and 31% had ascites at baseline. Seventy-three percent had a platinum-free interval (PFI) of 3 months to 6 months and 27% had PFI of <3 months. ECOG performance status was 0 for 59%, 1 for 34% and 2 for 7% of the patients.

The addition of bevacizumab to chemotherapy demonstrated a statistically significant improvement in investigator-assessed PFS, which was supported by a retrospective independent review analysis. Results for the ITT population are presented in Table 10 and Figure 6. Results for the separate chemotherapy cohorts are presented in Table 11.

Table 10: Efficacy Results in Study MO22224
Efficacy Parameter | Bevacizumabwith Chemotherapy (N=179) | Chemotherapy (N=182)
Progression-Free Survival per Investigator
Median (95% CI), in months | 6.8 (5.6, 7.8) | 3.4 (2.1, 3.8)
HR (95% CI)a | 0.38 (0.30, 0.49)
p-value b | <0.0001
Overall Survival
Median (95% CI), in months | 16.6 (13.7, 19.0) | 13.3 (11.9, 16.4)
HR (95% CI)a | 0.89 (0.69, 1.14)
Overall Response Rate
Number of Patients with Measurable Disease at Baseline | 142 | 144
Rate, % (95% CI) | 28% (21%, 36%) | 13% (7%, 18%)
Duration of Response
Median, in months | 9.4 | 5.4
a per stratified Cox proportional hazards model
b per stratified log-rank test

Figure 6: Kaplan-Meier Curves for Investigator-Assessed Progression-Free Survival in Platinum-Resistant Recurrent Epithelial Ovarian, Fallopian Tube, or Primary Peritoneal Cancer in Study MO22224

Table 11: Efficacy Results in Study MO22224 by Chemotherapy
Efficacy Parameter | Paclitaxel |  | Topotecan |  | Pegylated Liposomal Doxorubicin
Efficacy Parameter | Bevacizumabwith Chemotherapy (N=60) | Chemotherapy (N=55) | Bevacizumabwith Chemotherapy (N=57) | Chemotherapy (N=63) | Bevacizumabwith Chemotherapy (N=62) | Chemotherapy (N=64)
Progression-Free Survival per Investigator
Median, in months (95% CI) | 9.6 (7.8, 11.5) | 3.9 (3.5, 5.5) | 6.2 (5.3, 7.6) | 2.1 (1.9, 2.3) | 5.1 (3.9, 6.3) | 3.5 (1.9, 3.9)
Hazard ratioa (95% CI) | 0.47 (0.31, 0.72) |  | 0.24 (0.15, 0.38) |  | 0.47 (0.32, 0.71)
Overall Survival
Median, in months (95% CI) | 22.4 (16.7, 26.7) | 13.2 (8.2, 19.7) | 13.8 (11.0, 18.3) | 13.3 (10.4, 18.3) | 13.7 (11.0, 18.3) | 14.1 (9.9, 17.8)
Hazard ratio a (95% CI) | 0.64 (0.41, 1.01) |  | 1.12 (0.73, 1.73) |  | 0.94 (0.63, 1.42)
Overall Response Rate
Number of patients with measurable disease at baseline | 45 | 43 | 46 | 50 | 51 | 51
Rate, % (95% CI) | 53 (39, 68) | 30 (17, 44) | 17 (6, 28) | 2 (0, 6) | 16 (6, 26) | 8 (0, 15)
Duration of Response
Median, in months | 11.6 | 6.8 | 5.2 | NE | 8.0 | 4.6
a per stratified Cox proportional hazards model
NE=Not Estimable

16 HOW SUPPLIED

Alymsys (bevacizumab-maly) injection is a clear to slightly opalescent, colorless to pale brown, sterile solution for intravenous infusion supplied in a carton containing single-dose vial in the following strengths and packaging configurations:

- 100 mg/4 mL (25 mg/mL): carton of one vial (NDC 85006-1754-1).
- 400 mg/16 mL (25 mg/mL): carton of one vial (NDC 85006-1755-1).

Store refrigerated at 2°C to 8°C (36°F to 46°F) in the original carton until time of use to protect from light. Do not freeze or shake the vial or carton.

17 PATIENT COUNSELING INFORMATION

Gastrointestinal Perforations and Fistulae: Bevacizumab products may increase the risk of developing gastrointestinal perforations and fistulae. Advise patients to immediately contact their health care provider for high fever, rigors, persistent or severe abdominal pain, severe constipation, or vomiting [see Warnings and Precautions (5.1)].

Surgery and Wound Healing Complications: Bevacizumab products can increase the risk of wound healing complications. Instruct patients not to undergo surgery without first discussing this potential risk with their health care provider [see Warnings and Precautions (5.2)].

Hemorrhage: Bevacizumab products can increase the risk of hemorrhage. Advise patients to immediately contact their health care provider for signs and symptoms of serious or unusual bleeding including coughing or spitting blood [see Warnings and Precautions (5.3)].

Arterial and Venous Thromboembolic Events: Bevacizumab products increase the risk of arterial and venous thromboembolic events. Advise patients to immediately contact their health care provider for signs and symptoms of arterial or venous thromboembolism [see Warnings and Precautions (5.4, 5.5)].

Hypertension: Bevacizumab products can increase blood pressure. Advise patients that they will undergo routine blood pressure monitoring and to contact their health care provider if they experience changes in blood pressure [see Warnings and Precautions (5.6)].

Posterior Reversible Leukoencephalopathy Syndrome: Posterior reversible encephalopathy syndrome (PRES) has been associated with bevacizumab products treatment. Advise patients to immediately contact their health care provider for new onset or worsening neurological function [see Warnings and Precautions (5.7)].

Renal Injury and Proteinuria: Bevacizumab products increase the risk of proteinuria and renal injury, including nephrotic syndrome. Advise patients that treatment with Alymsys requires regular monitoring of renal function and to contact their health care provider for proteinuria or signs and symptoms of nephrotic syndrome [see Warnings and Precautions (5.8)].

Infusion-Related Reactions: Bevacizumab products can cause infusion-related reactions. Advise patients to contact their health care provider immediately for signs or symptoms of infusion-related reactions [see Warnings and Precautions (5.9)].

Congestive Heart Failure: Bevacizumab products can increase the risk of developing congestive heart failure. Advise patients to contact their health care provider immediately for signs and symptoms of CHF [see Warnings and Precautions (5.12)].

Embryo-Fetal Toxicity: Advise female patients that bevacizumab products may cause fetal harm and to inform their health care provider with a known or suspected pregnancy [see Warnings and Precautions (5.10), Use in Specific Populations (8.1)]. Advise females of reproductive potential to use effective contraception during treatment with Alymsys and for 6 months after the last dose [see Use in Specific Populations (8.3)].

Ovarian Failure: Bevacizumab products may lead to ovarian failure. Advise patients of potential options for preservation of ova prior to starting treatment [see Warnings and Precautions (5.11)].

Lactation: Advise women not to breastfeed during treatment with Alymsys and for 6 months after the last dose [see Use in Specific Populations (8.2)].

Manufactured by:

Amneal Pharmaceuticals LLC

Bridgewater, NJ 08807

Product of Spain

US License No. 2241

Distributed by:

Valorum Biologics, LLC

New York, NY 10022

Rev. 01-2026-00